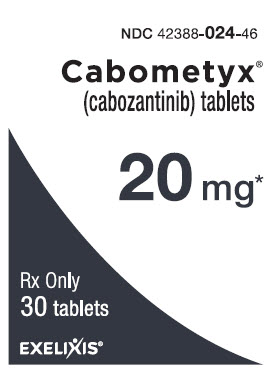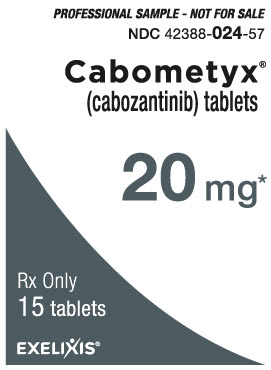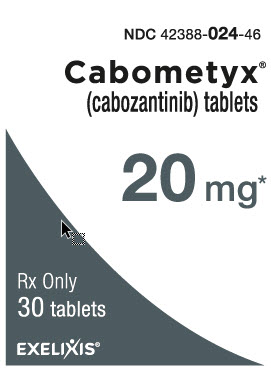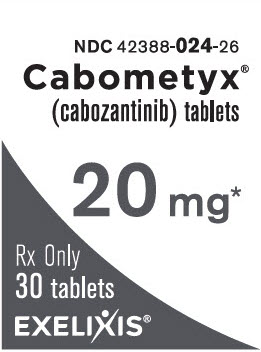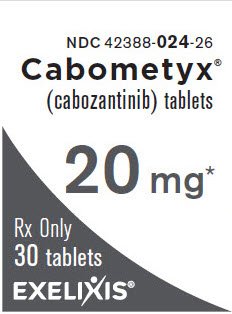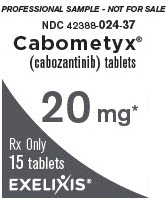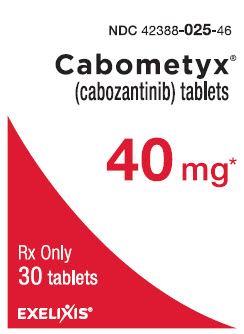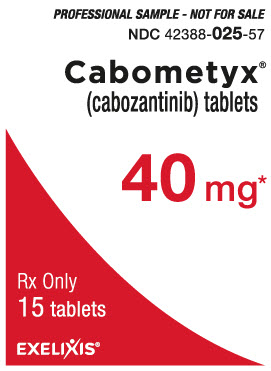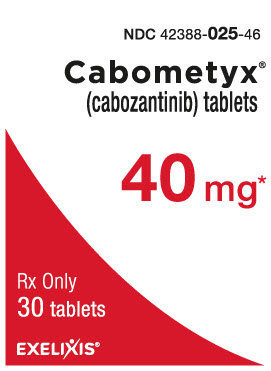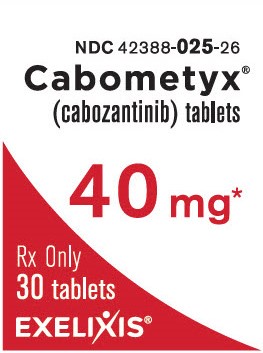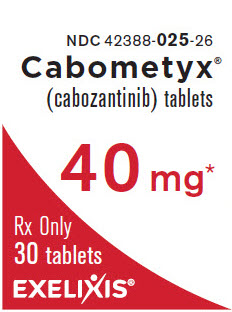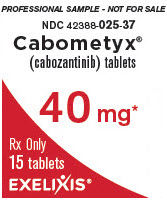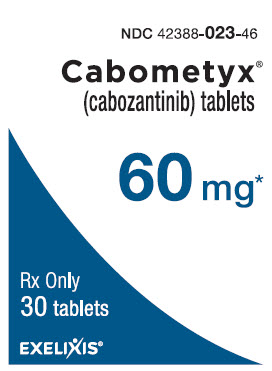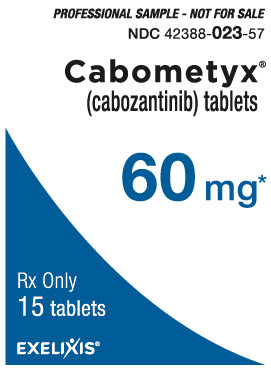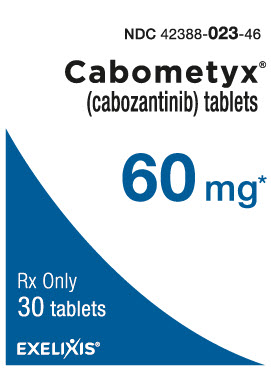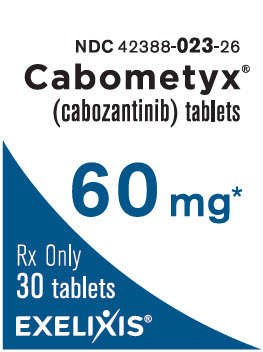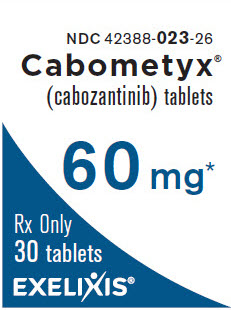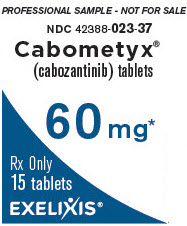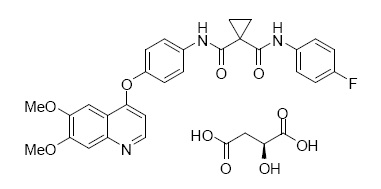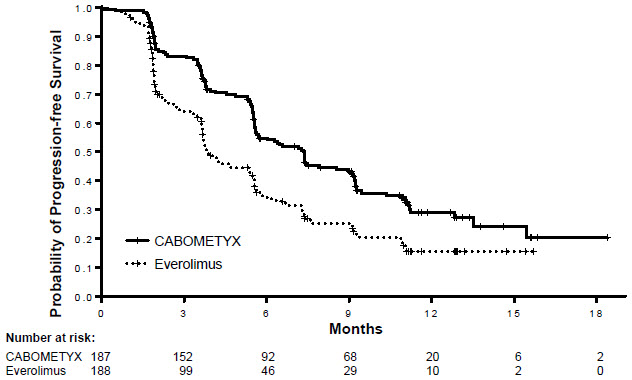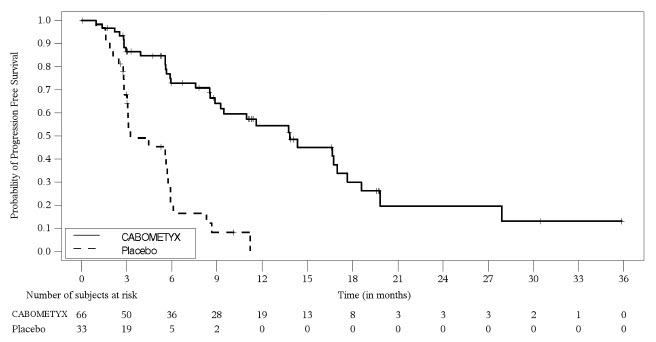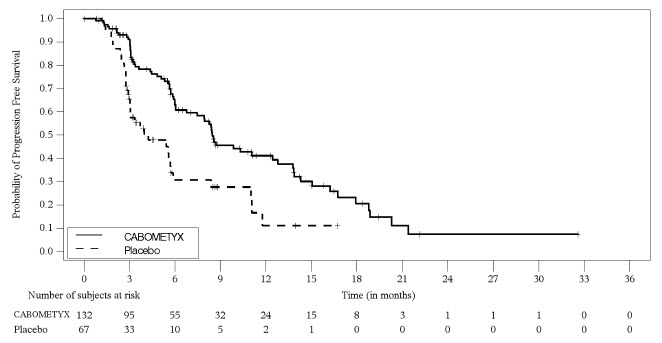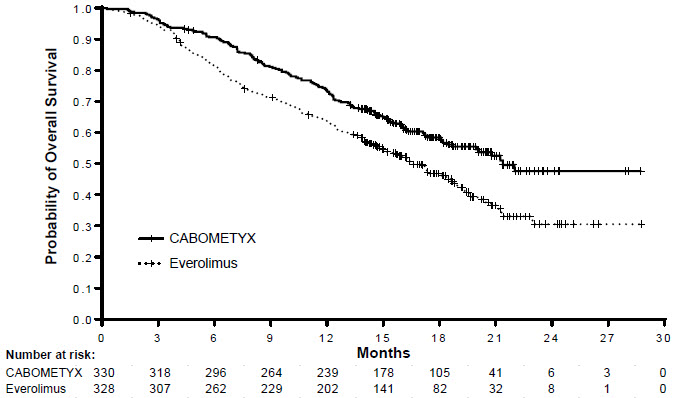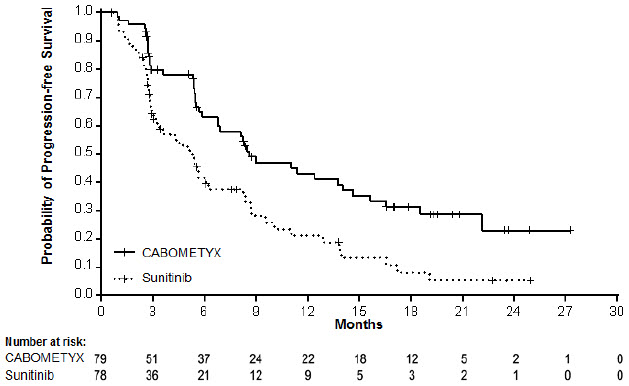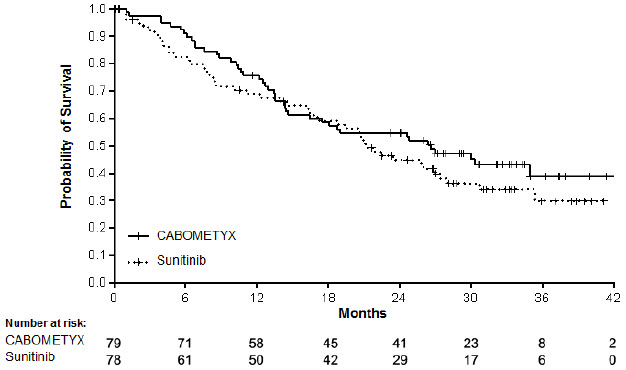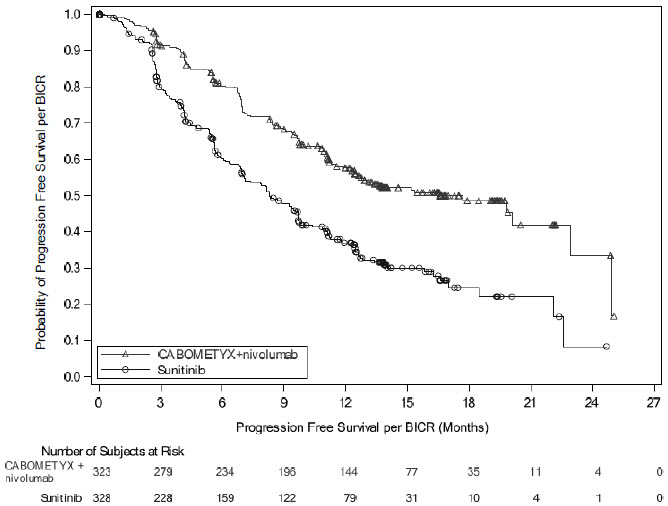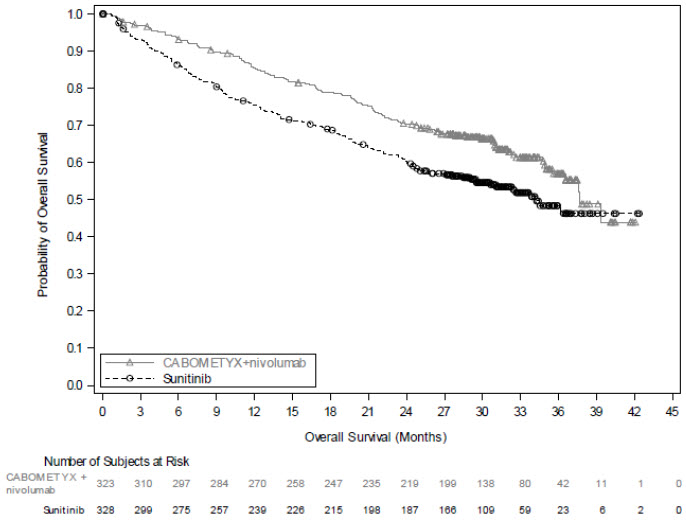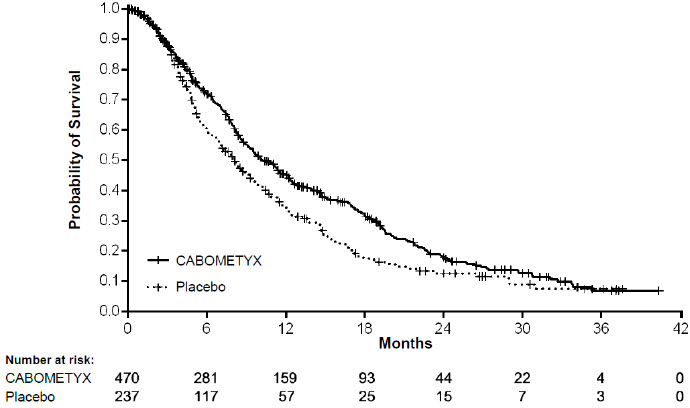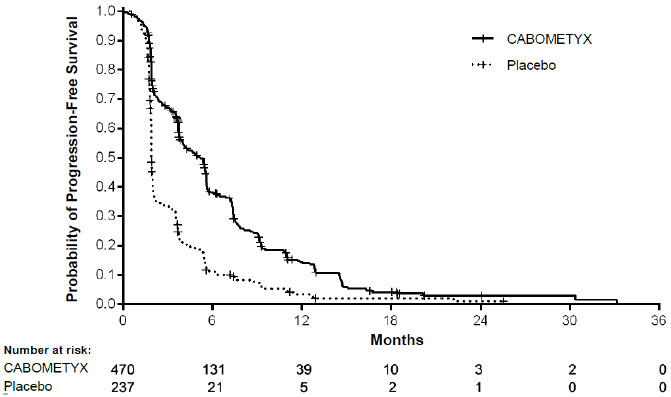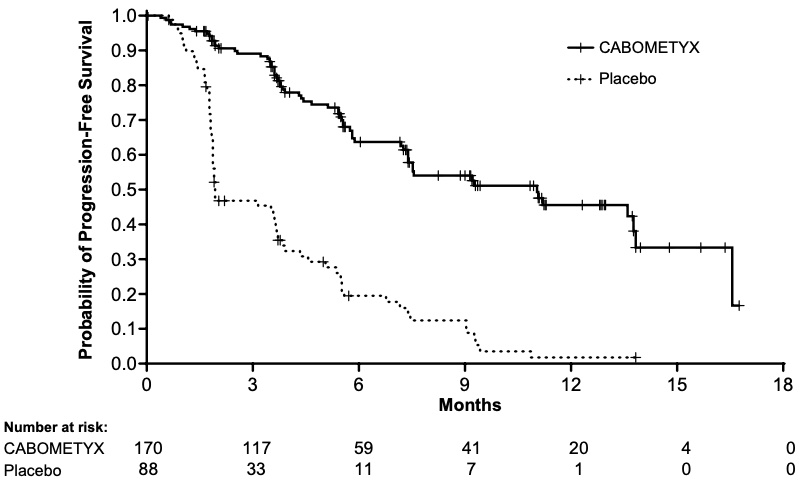 DRUG LABEL: CABOMETYX
NDC: 42388-023 | Form: TABLET
Manufacturer: Exelixis, Inc.
Category: prescription | Type: HUMAN PRESCRIPTION DRUG LABEL
Date: 20251019

ACTIVE INGREDIENTS: cabozantinib s-malate 60 mg/1 1
INACTIVE INGREDIENTS: CELLULOSE, MICROCRYSTALLINE; ANHYDROUS LACTOSE; HYDROXYPROPYL CELLULOSE (1600000 WAMW); CROSCARMELLOSE SODIUM; SILICON DIOXIDE; MAGNESIUM STEARATE; HYPROMELLOSES; TITANIUM DIOXIDE; TRIACETIN; FERRIC OXIDE YELLOW

HIGHLIGHTS OF PRESCRIBING INFORMATION

These highlights do not include all the information needed to use CABOMETYX safely and effectively. See full prescribing information for CABOMETYX.
CABOMETYX® (cabozantinib) tablets, for oral use
Initial U.S. Approval: 2012

RECENT MAJOR CHANGES

Indications and Usage, Neuroendocrine Tumors (1.4) 03/2025
Dosage and Administration, Recommended Dosage for NET (2.4) 03/2025
Warnings and Precautions (5.4) 03/2025
Dosage and Administration, Recommended Dosage (2.2) 09/2025
Warnings and Precautions (5.5) 10/2025

1 INDICATIONS AND USAGE

CABOMETYX is a kinase inhibitor indicated for the treatment of

- patients with advanced renal cell carcinoma (RCC). (1.1)
- patients with advanced renal cell carcinoma, as a first-line treatment in combination with nivolumab (1.1)
- patients with hepatocellular carcinoma (HCC) who have been previously treated with sorafenib (1.2)
- adult and pediatric patients 12 years of age and older with locally advanced or metastatic differentiated thyroid cancer (DTC) that has progressed following prior VEGFR-targeted therapy and who are radioactive iodine-refractory or ineligible (1.3)
- adult and pediatric patients 12 years of age and older with previously treated, unresectable, locally advanced or metastatic, well-differentiated pancreatic neuroendocrine tumors (pNET). (1.4)
- adult and pediatric patients 12 years of age and older with previously treated, unresectable, locally advanced or metastatic, well-differentiated extra-pancreatic neuroendocrine tumors (epNET). (1.4)

2 DOSAGE AND ADMINISTRATION

- Do NOT substitute CABOMETYX tablets with cabozantinib capsules. (2.1)
- Administer on an empty stomach at least 1 hour before or at least 2 hours after eating. (2.2)
- Stop treatment with CABOMETYX at least 3 weeks prior to scheduled surgery, including dental surgery. (2.1)
- Recommended Dose:
  - RCC (Single Agent): 60 mg orally, once daily. (2.2)
  - RCC (Combination Therapy): 40 mg orally, once daily with:
    - 240 mg nivolumab every 2 weeks by intravenous infusion; -OR-
    - 480 mg nivolumab every 4 weeks by intravenous infusion; -OR-
    - 600 mg nivolumab and 10,000 units hyaluronidase every 2 weeks administered subcutaneously; -OR-
    - 1,200 mg nivolumab and 20,000 units hyaluronidase every 4 weeks administered subcutaneously. (2.2)
  - HCC: 60 mg orally, once daily. (2.2)
  - DTC, pNET, epNET
    - Adult patients and pediatric patients 12 years of age and older with bodyweight greater than or equal to 40 kg: 60 mg orally once daily. (2.2)
    - Pediatric patients 12 years of age and older with bodyweight less than 40 kg: 40 mg orally once daily. (2.2)

3 DOSAGE FORMS AND STRENGTHS

Tablets: 60 mg, 40 mg, 20 mg. (3)

4 CONTRAINDICATIONS

None (4)

5 WARNINGS AND PRECAUTIONS

- Hemorrhage: Do not administer CABOMETYX if recent history of hemorrhage. (5.1)
- Perforations and Fistulas: Monitor for symptoms. Discontinue CABOMETYX for Grade 4 fistula or perforation. (5.2)
- Thromboembolic Events: Discontinue CABOMETYX for myocardial infarction or serious venous or arterial thromboembolic events. (5.3)
- Hypertension and Hypertensive Crisis: Monitor blood pressure regularly. Interrupt for hypertension that is not adequately controlled with anti-hypertensive therapy. Discontinue CABOMETYX for hypertensive crisis or severe hypertension that cannot be controlled with anti-hypertensive therapy. (5.4)
- Cardiac Failure: Monitor patients for signs and symptoms of cardiac failure throughout treatment. (5.5)
- Diarrhea: May be severe. Interrupt CABOMETYX until diarrhea resolves or decreases to ≤Grade 1, resume at reduced dose. Recommend standard antidiarrheal treatments. (5.6)
- Palmar-Plantar Erythrodysesthesia (PPE): Interrupt CABOMETYX treatment until PPE resolves or decreases to Grade 1. (5.7)
- Hepatotoxicity: When used in combination with nivolumab, higher frequencies of Grade 3 and 4 ALT and AST elevation may occur than with CABOMETYX alone. Monitor liver enzymes before initiation of and periodically throughout treatment. Consider withholding CABOMETYX and/or nivolumab, initiating corticosteroid therapy, and/or permanently discontinuing the combination for severe or life- threatening hepatotoxicity. (5.8)
- Adrenal Insufficiency: When used in combination with nivolumab, primary or secondary adrenal insufficiency may occur. For Grade 2 or higher adrenal insufficiency, initiate symptomatic treatment, including hormone replacement as clinically indicated. Withhold CABOMETYX and/or nivolumab depending on severity. (5.9)
- Proteinuria: Monitor urine protein. Interrupt CABOMETYX until proteinuria resolves to ≤ Grade 1, resume CABOMETYX at a reduced dose. Discontinue for nephrotic syndrome. (5.10)
- Osteonecrosis of the jaw (ONJ): Withhold CABOMETYX for at least 3 weeks prior to invasive dental procedures and for development of ONJ. (5.11)
- Impaired Wound Healing: Withhold CABOMETYX for at least 3 weeks before elective surgery. Do not administer for at least 2 weeks following major surgery and adequate wound healing. The safety of resumption of CABOMETYX after resolution of wound healing complications has not been established. (5.12)
- Reversible Posterior Leukoencephalopathy Syndrome (RPLS): Discontinue CABOMETYX. (5.13)
- Thyroid Dysfunction: Monitor thyroid function before and during treatment with CABOMETYX. (5.14)
- Hypocalcemia: Withhold CABOMETYX and resume at reduced dose upon recovery or permanently discontinue CABOMETYX depending on severity. (5.15)
- Embryo-Fetal Toxicity: Can cause fetal harm. Advise females of reproductive potential of the potential risk to a fetus and to use effective contraception. (5.16, 8.1, 8.3)

6 ADVERSE REACTIONS

The most common (≥ 20%) adverse reactions are:

- as a single agent: diarrhea, fatigue, PPE, decreased appetite, hypertension, nausea, vomiting, weight decreased, constipation. (6.1)
- in combination with nivolumab: diarrhea, fatigue, hepatotoxicity, PPE, stomatitis, rash, hypertension, hypothyroidism, musculoskeletal pain, decreased appetite, nausea, dysgeusia, abdominal pain, cough, and upper respiratory tract infection. (6.1)

To report SUSPECTED ADVERSE REACTIONS, contact Exelixis, Inc. at 1-855-500-3935 or FDA at 1-800-FDA-1088 or www.fda.gov/medwatch.

7 DRUG INTERACTIONS

- Strong CYP3A4 inhibitors: Reduce the CABOMETYX dosage if coadministration cannot be avoided. (2.4, 7.1)
- Strong or moderate CYP3A4 inducers: Increase the CABOMETYX dosage if coadministration cannot be avoided. (2.5, 7.1)

8 USE IN SPECIFIC POPULATIONS

- Hepatic Impairment: Reduce the CABOMETYX dosage for patients with moderate hepatic impairment. Avoid in patients with severe hepatic impairment. (2.6, 8.6)
- Lactation: Advise not to breastfeed. (8.2)
- Pediatric Use: Monitor open growth plates in adolescent patients. Consider interrupting or discontinuing CABOMETYX if abnormalities occur. (8.4)

FULL PRESCRIBING INFORMATION

1 INDICATIONS AND USAGE

1.1 Renal Cell Carcinoma

CABOMETYX is indicated for the treatment of patients with advanced renal cell carcinoma (RCC).

CABOMETYX, in combination with nivolumab, is indicated for the first-line treatment of patients with advanced RCC.

1.2 Hepatocellular Carcinoma

CABOMETYX is indicated for the treatment of patients with hepatocellular carcinoma (HCC) who have been previously treated with sorafenib.

1.3 Differentiated Thyroid Cancer

CABOMETYX is indicated for the treatment of adult and pediatric patients 12 years of age and older with locally advanced or metastatic differentiated thyroid cancer (DTC) that has progressed following prior VEGFR-targeted therapy and who are radioactive iodine-refractory or ineligible.

1.4 Neuroendocrine Tumors

CABOMETYX is indicated for the treatment of adult and pediatric patients 12 years of age and older with previously treated, unresectable, locally advanced or metastatic, well-differentiated pancreatic neuroendocrine tumors (pNET).

CABOMETYX is indicated for the treatment of adult and pediatric patients 12 years of age and older with previously treated, unresectable, locally advanced or metastatic, well-differentiated extra-pancreatic neuroendocrine tumors (epNET).

2 DOSAGE AND ADMINISTRATION

2.1 Important Dosage Information and Recommended Evaluation and Testing Before Initiating CABOMETYX

- Do not substitute CABOMETYX tablets with cabozantinib capsules.
- Stop treatment with CABOMETYX 3 weeks prior to scheduled surgery, including dental surgery to reduce the risk of hemorrhage. Do not administer CABOMETYX for at least 2 weeks after major surgery and until adequate wound healing [see Warnings and Precautions (5.1, 5.11, 5.12)].

2.2 Recommended Dosage

Administer CABOMETYX on an empty stomach. Administer at least 1 hour before or at least 2 hours after eating [see Clinical Pharmacology (12.3)].

Swallow CABOMETYX tablets whole. Do not crush, chew, or split CABOMETYX tablets.

Do not take a missed dose within 12 hours of the next dose.

Modify the CABOMETYX dose for patients taking drugs known to moderately or strongly induce CYP3A4 or strongly inhibit CYP3A4 and for patients with moderate hepatic impairment [see Dosage and Administration (2.4, 2.5, 2.6)].

The recommended dosages of CABOMETYX are presented in Table 1.

Table 1. Recommended Dosage for CABOMETYX
Indication | Recommended Dosage | Duration
Renal Cell Carcinoma | Single Agent 60 mg orally once daily | Until disease progression or unacceptable toxicity
Renal Cell Carcinoma | Combination Therapy 40 mg orally once daily in combination with:; - 240 mg nivolumab every 2 weeks (30- minute intravenous infusion); -OR- - 480 mg nivolumab every 4 weeks (30- minute intravenous infusion); -OR- - 600 mg nivolumab and 10,000 units hyaluronidase administered subcutaneously over approximately 3-5 minutes every 2 weeks; -OR- - 1,200 mg nivolumab and 20,000 units hyaluronidase administered subcutaneously over approximately 3-5 minutes every 4 weeks
Renal Cell Carcinoma | Combination Therapy 40 mg orally once daily in combination with:; - 240 mg nivolumab every 2 weeks (30- minute intravenous infusion); -OR- - 480 mg nivolumab every 4 weeks (30- minute intravenous infusion); -OR- - 600 mg nivolumab and 10,000 units hyaluronidase administered subcutaneously over approximately 3-5 minutes every 2 weeks; -OR- - 1,200 mg nivolumab and 20,000 units hyaluronidase administered subcutaneously over approximately 3-5 minutes every 4 weeks | CABOMETYX Until disease progression or unacceptable toxicity
 | Combination Therapy 40 mg orally once daily in combination with:; - 240 mg nivolumab every 2 weeks (30- minute intravenous infusion); -OR- - 480 mg nivolumab every 4 weeks (30- minute intravenous infusion); -OR- - 600 mg nivolumab and 10,000 units hyaluronidase administered subcutaneously over approximately 3-5 minutes every 2 weeks; -OR- - 1,200 mg nivolumab and 20,000 units hyaluronidase administered subcutaneously over approximately 3-5 minutes every 4 weeks | Nivolumab -OR- nivolumab and hyaluronidase Until disease progression or unacceptable toxicity for up to 2 years
Hepatocellular Carcinoma | 60 mg orally once daily | Until disease progression or unacceptable toxicity
Differentiated Thyroid Cancer and Neuroendocrine Tumors | Adult Patients and Pediatric Patients 12 years of age and older with bodyweight greater than or equal to 40 kg: 60 mg orally once daily Pediatric patients 12 years of age and older with bodyweight less than 40 kg: 40 mg orally once daily | Until disease progression or unacceptable toxicity

2.3 Dosage Modifications for Adverse Reactions

Withhold CABOMETYX for:

- Intolerable Grade 2 adverse reactions
- Grade 3 or 4 adverse reactions
- Osteonecrosis of the jaw

Upon resolution/improvement (i.e., return to baseline or resolution to Grade 1) of an adverse reaction, reduce the dose as follows:

Table 2. Recommended Dosage Reductions for CABOMETYX for Adverse Reactions
Recommended Dosage | First Dosage Reduction To | Second Dosage Reduction To
CABOMETYX 60 mg daily in adult and pediatric patients 12 years of age and older with bodyweight greater than or equal to 40 kg | 40 mg daily | 20 mg daily [If previously receiving lowest dose, resume at same dose. If lowest dose not tolerated, discontinue CABOMETYX.]
CABOMETYX 40 mg daily in pediatric patients 12 years of age and older with bodyweight less than 40 kg | 20 mg daily | 20 mg every other day
CABOMETYX 40 mg daily in combination with nivolumab | 20 mg daily | 20 mg every other day

Table 3. Recommended Dosage Modifications for CABOMETYX Adverse Reactions
Adverse Reaction | Severity [Graded according to National Cancer Institute Common Terminology Criteria for Adverse Events (NCI CTCAE version 5.0)] | CABOMETYX Dosage Modification
Hemorrhage [see Warnings and Precautions (5.1)] | Grade 3 or 4 | - Permanently discontinue CABOMETYX
Perforations and Fistulas [see Warnings and Precautions (5.2)] | Any grade gastrointestinal perforation or Grade 4 fistula | - Permanently discontinue CABOMETYX
Thromboembolic Events [see Warnings and Precautions (5.3)] | Any grade acute myocardial infarction or Grade 2 or higher cerebral infarction or Grade 3 or 4 arterial thromboembolic events or Grade 4 venous thromboembolic events | - Permanently discontinue CABOMETYX
Hypertension and Hypertensive Crisis [see Warnings and Precautions (5.4)] | Grade 3 | - Withhold CABOMETYX until hypertension is adequately controlled to ≤Grade 2 - Resume at reduced dose - Permanently discontinue CABOMETYX for hypertension that cannot be controlled
Hypertension and Hypertensive Crisis [see Warnings and Precautions (5.4)] | Grade 4 | - Permanently discontinue CABOMETYX
Diarrhea [see Warnings and Precautions (5.6)] | Grade 2, Grade 3, or Grade 4 | - Withhold CABOMETYX until ≤Grade 1 - Resume at reduced dose
Palmar-Plantar Erythrodysesthesia [see Warnings and Precautions (5.7)] | Intolerable Grade 2 or Grade 3 | - Withhold CABOMETYX until ≤Grade 1 - Resume at reduced dose
Proteinuria [see Warnings and Precautions (5.10)] | Grade 2 or 3 | - Withhold CABOMETYX until improvement to ≤ Grade 1 proteinuria - Resume at a reduced dose - Permanently discontinue CABOMETYX for nephrotic syndrome
Osteonecrosis of the jaw (ONJ) [see Warnings and Precautions (5.11)] | Any grade | - Withhold CABOMETYX for development of ONJ until complete resolution - Resume at reduced dose
Reversible Posterior Leukoencephalopathy Syndrome [see Warnings and Precautions (5.13)] | Any grade | - Permanently discontinue CABOMETYX
Other Adverse Reactions [see Adverse Reactions (6.1)] | Intolerable Grade 2, or Grade 3, or Grade 4 | - Withhold CABOMETYX until improvement to baseline or ≤Grade 1 - Resume at reduced dose or permanently discontinue depending on severity

The following table represents dosage modifications for the drug administered in combination that are different from those described above for CABOMETYX or in the Full Prescribing Information:

Table 4. Recommended Specific Dosage Modifications for Hepatic Adverse Reactions for Combination
CABOMETYX in combination with nivolumab | ALT or AST >3 times ULN but ≤10 times ULN with concurrent total bilirubin <2 times ULN | Withhold [Consider corticosteroid therapy for hepatic adverse reactions if CABOMETYX is withheld or discontinued when administered in combination with nivolumab] both CABOMETYX and nivolumab until adverse reactions recover [After recovery, rechallenge with one or both of CABOMETYX and nivolumab may be considered. If rechallenging with nivolumab with or without CABOMETYX, refer to nivolumab Prescribing Information.] to Grades 0 or 1
 | ALT or AST >10 times ULN or >3 times ULN with concurrent total bilirubin ≥2 times ULN | Permanently discontinue both CABOMETYX and nivolumab

When administering CABOMETYX in combination with nivolumab for the treatment of advanced RCC, refer to the nivolumab prescribing information.

2.4 Dosage Modifications for Coadministration with Strong CYP3A4 Inhibitors

Reduce the daily CABOMETYX dose by 20 mg (for example, from 60 mg to 40 mg daily or from 40 mg to 20 mg daily or from 20 mg daily to 20 mg every other day in pediatric patients 12 years of age and older with bodyweight less than 40 kg). Resume the dose that was used prior to initiating the strong CYP3A4 inhibitor 2 to 3 days after discontinuation of the strong inhibitor [see Drug Interactions (7.1), Clinical Pharmacology (12.3)].

2.5 Dosage Modifications for Coadministration with Strong or Moderate CYP3A4 Inducers

Increase the daily CABOMETYX dose by 20 mg (for example, from 60 mg to 80 mg daily or from 40 mg to 60 mg daily) as tolerated. Resume the dose that was used prior to initiating the strong or moderate CYP3A4 inducer 2 to 3 days after discontinuation of the inducer. Do not exceed a daily dose of 80 mg [see Drug Interactions (7.1), Clinical Pharmacology (12.3)].

2.6 Dosage Modifications for Patients with Hepatic Impairment

Reduce the starting dose of CABOMETYX 60 mg daily to 40 mg daily or 40 mg daily to 20 mg daily (for pediatric patients 12 years of age and older with bodyweight less than 40 kg) in patients with moderate hepatic impairment (Child-Pugh B) [see Use in Specific Populations (8.6), Clinical Pharmacology (12.3)].

3 DOSAGE FORMS AND STRENGTHS

Tablets:

- 60 mg: yellow film-coated, oval shaped with no score, and debossed with "XL" on one side and "60" on the other side.
- 40 mg: yellow film-coated, triangle shaped with no score, and debossed with "XL" on one side and "40" on the other side.
- 20 mg: yellow film-coated, round with no score, and debossed with "XL" on one side and "20" on the other side.

4 CONTRAINDICATIONS

None.

5 WARNINGS AND PRECAUTIONS

5.1 Hemorrhage

CABOMETYX can cause severe and fatal hemorrhages. Do not administer CABOMETYX to patients who have a recent history of hemorrhage, including hemoptysis, hematemesis, or melena.

The incidence of Grade 3 to 5 hemorrhagic events was 5% in CABOMETYX-treated patients in RCC, HCC, and DTC studies [see Adverse Reactions (6.1)].

Withhold CABOMETYX for 3 weeks prior to scheduled surgery, including dental surgery to reduce the risk of hemorrhage. Permanently discontinue CABOMETYX for Grade 3 or 4 hemorrhage and prior to surgery as recommended [see Dosage and Administration (2.3), Warnings and Precautions (5.11, 5.12)].

5.2 Perforations and Fistulas

CABOMETYX can cause gastrointestinal (GI) perforations and fistulas.

Fistulas, including fatal cases, occurred in 1% of CABOMETYX-treated patients [see [see Adverse Reactions (6.1)]. GI perforations, including fatal cases, occurred in 1% of CABOMETYX-treated patients.

Monitor patients for signs and symptoms of fistulas and perforations, including abscess and sepsis. Discontinue CABOMETYX in patients who experience a Grade 4 fistula or a GI perforation [see Dosage and Administration (2.3)].

5.3 Thromboembolic Events

CABOMETYX can cause arterial or venous thromboembolic events.

Venous thromboembolism occurred in 7% (including 4% pulmonary embolism) and arterial thromboembolism occurred in 2% of CABOMETYX-treated patients. Fatal thromboembolic events occurred in CABOMETYX-treated patients [see Adverse Reactions (6.1)].

Discontinue CABOMETYX in patients who develop an acute myocardial infarction or serious arterial or venous thromboembolic events that require medical intervention [see Dosage and Administration (2.3)].

5.4 Hypertension and Hypertensive Crisis

CABOMETYX can cause hypertension, including hypertensive crisis [see Adverse Reactions (6.1)]. Hypertension was reported in 37% (16% Grade 3 and <1% Grade 4) of CABOMETYX-treated patients. In CABINET (n=195) [see Clinical Studies (14.4)], hypertension was reported in 65% (26% Grade 3) of CABOMETYX-treated patients.

Do not initiate CABOMETYX in patients with uncontrolled hypertension. Monitor blood pressure regularly during CABOMETYX treatment. Withhold CABOMETYX for hypertension that is not adequately controlled with medical management; when controlled, resume CABOMETYX at a reduced dose [see Dosage and Administration (2.3)]. Permanently discontinue CABOMETYX for severe hypertension that cannot be controlled with anti-hypertensive therapy or for hypertensive crisis [see Dosage and Administration (2.3)].

5.5 Cardiac Failure

CABOMETYX can cause severe and fatal cardiac failure [see Adverse Reactions (6.1)]. Cardiac failure occurred in 0.5% of patients treated with CABOMETYX as a single agent, including fatal cardiac failure in 0.1% of patients. Median time to onset of cardiac failure was 73 days (range: 44 days to 159 days).

Consider baseline and periodic evaluations of left ventricular ejection fraction. Monitor for signs and symptoms of cardiovascular events. Withhold and resume at a reduced dose upon recovery or permanently discontinue CABOMETYX depending on the severity [see Dosage and Administration (2.3)].

5.6 Diarrhea

CABOMETYX can cause diarrhea. Diarrhea occurred in 62% of patients treated with CABOMETYX. Grade 3 diarrhea occurred in 10% of patients treated with CABOMETYX [see Adverse Reactions (6.1)].

Monitor and manage patients using antidiarrheals as indicated. Withhold CABOMETYX until improvement to ≤Grade 1, resume CABOMETYX at a reduced dose [see Dosage and Administration (2.3)].

5.7 Palmar-Plantar Erythrodysesthesia

CABOMETYX can cause palmar-plantar erythrodysesthesia (PPE). PPE occurred in 45% of patients treated with CABOMETYX [see Adverse Reactions (6.1)]. Grade 3 PPE occurred in 13% of patients treated with CABOMETYX.

Withhold CABOMETYX until improvement to Grade 1 and resume CABOMETYX at a reduced dose for intolerable Grade 2 PPE or Grade 3 PPE [see Dosage and Administration (2.3)].

5.8 Hepatotoxicity

CABOMETYX in combination with nivolumab can cause hepatic toxicity with higher frequencies of Grades 3 and 4 ALT and AST elevations compared to CABOMETYX alone.

Monitor liver enzymes before initiation of and periodically throughout treatment. Consider more frequent monitoring of liver enzymes as compared to when the drugs are administered as single agents. For elevated liver enzymes, interrupt CABOMETYX and nivolumab and consider administering corticosteroids [see Dosage and Administration (2.3)].

With the combination of CABOMETYX and nivolumab, Grades 3 and 4 increased ALT or AST were seen in 11% of patients [see Adverse Reactions (6.1)]. ALT or AST >3 times ULN (Grade ≥2) was reported in 83 patients, of whom 23 (28%) received systemic corticosteroids; ALT or AST resolved to Grades 0-1 in 74 (89%). Among the 44 patients with Grade ≥2 increased ALT or AST who were rechallenged with either CABOMETYX (n=9) or nivolumab (n=11) as a single agent or with both (n=24), recurrence of Grade ≥2 increased ALT or AST was observed in 2 patients receiving CABOMETYX, 2 patients receiving nivolumab, and 7 patients receiving both CABOMETYX and nivolumab.

Withhold and then resume CABOMETYX at a reduced dose based on severity [see Dosage and Administration (2.3)].

5.9 Adrenal Insufficiency

CABOMETYX in combination with nivolumab can cause primary or secondary adrenal insufficiency.

Adrenal insufficiency occurred in 4.7% (15/320) of patients treated with the combination of CABOMETYX and nivolumab including Grade 3 (2.2%), and Grade 2 (1.9%) adverse reactions [see Adverse Reactions (6.1)]. Adrenal insufficiency led to permanent discontinuation of CABOMETYX and nivolumab in 0.9% and withholding of CABOMETYX and nivolumab in 2.8% of patients with RCC.

Approximately 80% (12/15) of patients with adrenal insufficiency received hormone replacement therapy, including systemic corticosteroids. Adrenal insufficiency resolved in 27% (n=4) of the 15 patients. Of the 9 patients in whom CABOMETYX with nivolumab was withheld for adrenal insufficiency, 6 reinstated treatment after symptom improvement; of these, all (n=6) received hormone replacement therapy and 2 had recurrence of adrenal insufficiency.

For Grade 2 or higher adrenal insufficiency, initiate symptomatic treatment, including hormone replacement as clinically indicated. Withhold CABOMETYX and/or nivolumab and resume CABOMETYX at a reduced dose depending on severity [see Dosage and Administration (2.3)].

5.10 Proteinuria

CABOMETYX can cause proteinuria.

Proteinuria was observed in 8% of patients receiving CABOMETYX [see Adverse Reactions (6.1)].

Monitor urine protein regularly during CABOMETYX treatment. For Grade 2 or 3 proteinuria, withhold CABOMETYX until improvement to ≤Grade 1 proteinuria, resume CABOMETYX at a reduced dose. Discontinue CABOMETYX in patients who develop nephrotic syndrome [see Dosage and Administration (2.3)].

5.11 Osteonecrosis of the Jaw

CABOMETYX can cause osteonecrosis of the jaw (ONJ).

ONJ occurred in <1% of patients treated with CABOMETYX [see Adverse Reactions (6.1)].

ONJ can manifest as jaw pain, osteomyelitis, osteitis, bone erosion, tooth or periodontal infection, toothache, gingival ulceration or erosion, persistent jaw pain or slow healing of the mouth or jaw after dental surgery. Perform an oral examination prior to initiation of CABOMETYX and periodically during CABOMETYX. Advise patients regarding good oral hygiene practices. Withhold CABOMETYX for at least 3 weeks prior to scheduled dental surgery or invasive dental procedures, if possible. Withhold CABOMETYX for development of ONJ until complete resolution, resume at a reduced dose [see Dosage and Administration (2.3)].

5.12 Impaired Wound Healing

CABOMETYX can cause impaired wound healing [see Adverse Reactions (6.1)]. Withhold CABOMETYX for at least 3 weeks prior to elective surgery [see Dosage and Administration (2.1)]. Do not administer CABOMETYX for at least 2 weeks after major surgery and until adequate wound healing. The safety of resumption of CABOMETYX after resolution of wound healing complications has not been established [see Dosage and Administration (2.1, 2.3)].

5.13 Reversible Posterior Leukoencephalopathy Syndrome

CABOMETYX can cause reversible Posterior Leukoencephalopathy Syndrome (RPLS), a syndrome of subcortical vasogenic edema diagnosed by characteristic finding on MRI. Perform an evaluation for RPLS in any patient presenting with seizures, headache, visual disturbances, confusion or altered mental function. Discontinue CABOMETYX in patients who develop RPLS [see Dosage and Administration (2.3)].

5.14 Thyroid Dysfunction

CABOMETYX can cause thyroid dysfunction, primarily hypothyroidism. Thyroid dysfunction occurred in 19% of patients treated with CABOMETYX, including Grade 3 in 0.4% of patients [see Adverse Reactions (6.1)].

Assess patients for signs of thyroid dysfunction prior to the initiation of CABOMETYX and monitor for signs and symptoms of thyroid dysfunction during CABOMETYX treatment. Thyroid function testing and management of dysfunction should be performed as clinically indicated [see Dosage and Administration (2.3)].

5.15 Hypocalcemia

CABOMETYX can cause hypocalcemia. Hypocalcemia occurred in 13% of patients treated with CABOMETYX, including Grade 3 in 2% and Grade 4 in 1% of patients [see Adverse Reactions (6.1)]. Laboratory abnormality data were not collected in CABOSUN and CABINET.

In COSMIC-311 (n=125) [see Clinical Studies (14.3)], hypocalcemia occurred in 36% of patients treated with CABOMETYX, including Grade 3 in 6% and Grade 4 in 3% of patients.

Monitor blood calcium levels and replace calcium as necessary during treatment. Withhold and resume at reduced dose upon recovery or permanently discontinue CABOMETYX depending on severity [see Dosage and Administration (2.3)].

5.16 Embryo-Fetal Toxicity

Based on data from animal studies and its mechanism of action, CABOMETYX can cause fetal harm when administered to a pregnant woman. Cabozantinib administration to pregnant animals during organogenesis resulted in embryolethality at exposures below those occurring clinically at the recommended dose, and in increased incidences of skeletal variations in rats and visceral variations and malformations in rabbits.

Advise pregnant women of the potential risk to a fetus. Advise females of reproductive potential to use effective contraception during treatment with CABOMETYX and for 4 months after the last dose [see Use in Specific Populations (8.1, 8.3), Clinical Pharmacology (12.1)].

6 ADVERSE REACTIONS

The following clinically significant adverse reactions are discussed elsewhere in the labeling:

- Hemorrhage [see Warnings and Precautions (5.1)]
- Perforations and Fistulas [see Warnings and Precautions (5.2)]
- Thromboembolic Events [see Warnings and Precautions (5.3)]
- Hypertension and Hypertensive Crisis [see Warnings and Precautions (5.4)]
- Cardiac Failure [see Warnings and Precautions (5.5)]
- Diarrhea [see Warnings and Precautions (5.6)]
- Palmar-plantar Erythrodysesthesia [see Warnings and Precautions (5.7)]
- Hepatotoxicity [see Warnings and Precautions (5.8)]
- Adrenal Insufficiency [see Warnings and Precautions (5.9)]
- Proteinuria [see Warnings and Precautions (5.10)]
- Osteonecrosis of the Jaw [see Warnings and Precautions (5.11)]
- Impaired Wound Healing [see Warnings and Precautions (5.12)]
- Reversible Posterior Leukoencephalopathy Syndrome [see Warnings and Precautions (5.13)]
- Thyroid Dysfunction [see Warnings and Precautions (5.14)]
- Hypocalcemia [see Warnings and Precautions (5.15)]

6.1 Clinical Trial Experience

Because clinical trials are conducted under widely varying conditions, adverse reaction rates observed in the clinical trials of a drug cannot be directly compared to rates in the clinical trials of another drug and may not reflect the rates observed in practice.

The data described in the WARNINGS AND PRECAUTIONS section and below reflect exposure to CABOMETYX as a single agent at 60 mg orally once daily until disease progression or unacceptable toxicity in 409 patients with RCC enrolled in a randomized, active-controlled trial (CABOSUN, METEOR), 467 patients with HCC enrolled in a randomized, placebo- controlled trial (CELESTIAL), 125 patients with DTC enrolled in a randomized, placebo- controlled trial (COSMIC-311), 195 patients with pNET or epNET enrolled in a randomized, placebo-controlled trial (CABINET), and at 40 mg CABOMETYX in combination with nivolumab 240 mg/m^2 every 2 weeks, in 320 patients with RCC enrolled in a randomized, active- controlled trial (CHECKMATE-9ER).

Renal Cell Carcinoma

METEOR

The safety of CABOMETYX was evaluated in METEOR, a randomized, open-label trial in which 331 patients with advanced renal cell carcinoma received CABOMETYX 60 mg once daily and 322 patients received everolimus 10 mg once daily until disease progression or unacceptable toxicity. Patients on both arms who had disease progression could continue treatment at the discretion of the investigator [see Clinical Studies (14)]. The median duration of treatment was 7.6 months (range 0.3 – 20.5) for patients receiving CABOMETYX and 4.4 months (range 0.21 – 18.9) for patients receiving everolimus.

Adverse reactions which occurred in ≥ 25% of CABOMETYX-treated patients, in order of decreasing frequency, were: diarrhea, fatigue, nausea, decreased appetite, palmar-plantar erythrodysesthesia (PPE), hypertension, vomiting, weight decreased, and constipation. Grade 3-4 adverse reactions and laboratory abnormalities which occurred in ≥ 5% of patients were hypertension, diarrhea, fatigue, PPE, hyponatremia, hypophosphatemia, hypomagnesemia, lymphopenia, anemia, hypokalemia, and increased GGT.

The dose was reduced in 60% of patients receiving CABOMETYX and in 24% of patients receiving everolimus. Twenty percent (20%) of patients received CABOMETYX 20 mg once daily as their lowest dose. The most frequent adverse reactions leading to dose reduction in patients treated with CABOMETYX were: diarrhea, PPE, fatigue, and hypertension. Adverse reactions leading to dose interruption occurred in 70% patients receiving CABOMETYX and in 59% patients receiving everolimus. Adverse reactions led to study treatment discontinuation in 10% of patients receiving CABOMETYX and in 10% of patients receiving everolimus. The most frequent adverse reactions leading to permanent discontinuation in patients treated with CABOMETYX were decreased appetite (2%) and fatigue (1%).

Table 5. Adverse Reactions Occurring in ≥ 10% Patients Who Received CABOMETYX in METEOR
Adverse Reaction | CABOMETYX (n=331) [One subject randomized to everolimus received cabozantinib.] |  | Everolimus (n=322)
Adverse Reaction | All Grades [National Cancer Institute (NCI) Common Terminology Criteria for Adverse Events (CTCAE) Version 4.0] | Grades 3-4 | All Grades | Grades 3-4
 | Percentage (%) of Patients
Gastrointestinal
Diarrhea | 74 | 11 | 28 | 2
Nausea | 50 | 4 | 28 | <1
Vomiting | 32 | 2 | 14 | <1
Stomatitis | 22 | 2 | 24 | 2
Constipation | 25 | <1 | 19 | <1
Abdominal pain [Includes the following terms: abdominal pain, abdominal pain upper, and abdominal pain lower] | 23 | 4 | 13 | 2
Dyspepsia | 12 | <1 | 5 | 0
General
Fatigue | 56 | 9 | 47 | 7
Mucosal inflammation | 19 | <1 | 23 | 3
Asthenia | 19 | 4 | 16 | 2
Metabolism and Nutrition
Decreased appetite | 46 | 3 | 34 | <1
Skin and Subcutaneous Tissue
Palmar-plantar erythrodysesthesia | 42 | 8 | 6 | <1
Rash [Includes the following terms: rash, rash erythematous, rash follicular, rash macular, rash papular, rash pustular, rash vesicular, genital rash, intermittent leg rash, rash on scrotum and penis, rash maculo- papular, rash pruritic, contact dermatitis, dermatitis acneiform] | 23 | <1 | 43 | <1
Dry skin | 11 | 0 | 10 | 0
Vascular
Hypertension [Includes the following terms hypertension, blood pressure increased, hypertensive crisis, blood pressure fluctuation] | 39 | 16 | 8 | 3
Investigations
Weight decreased | 31 | 2 | 12 | 0
Nervous System
Dysgeusia | 24 | 0 | 9 | 0
Headache | 11 | <1 | 12 | <1
Dizziness | 11 | 0 | 7 | 0
Endocrine
Hypothyroidism | 21 | 0 | <1 | <1
Respiratory, Thoracic, and Mediastinal
Dysphonia | 20 | <1 | 4 | 0
Dyspnea | 19 | 3 | 29 | 4
Cough | 18 | <1 | 33 | <1
Blood and Lymphatic
Anemia | 17 | 5 | 38 | 16
Musculoskeletal and Connective Tissue
Pain in extremity | 14 | 1 | 8 | <1
Muscle spasms | 13 | 0 | 5 | 0
Arthralgia | 11 | <1 | 14 | 1
Renal and Urinary
Proteinuria | 12 | 2 | 9 | <1

Other clinically relevant adverse reactions (all grades) that were reported in <10% of patients treated with CABOMETYX included: wound complications (2%), cardiac failure (<1%), convulsion (<1%), pancreatitis (<1%), osteonecrosis of the jaw (<1%), and hepatitis cholestatic (<1%).

Table 6. Laboratory Abnormalities Occurring in ≥ 25% Patients Who Received CABOMETYX in METEOR
Laboratory Abnormality | CABOMETYX (n=331) |  | Everolimus (n=322)
Laboratory Abnormality | All Grades | Grade 3-4 | All Grades | Grade 3-4
 | Percentage (%) of Patients
Chemistry
Increased AST | 74 | 3 | 40 | <1
Increased ALT | 68 | 3 | 32 | <1
Increased creatinine | 58 | <1 | 71 | 0
Increased triglycerides | 53 | 4 | 73 | 13
Hypophosphatemia | 48 | 8 | 36 | 5
Hyperglycemia | 37 | 2 | 59 | 8
Hypoalbuminemia | 36 | 2 | 28 | <1
Increased ALP | 35 | 2 | 29 | 1
Hypomagnesemia | 31 | 7 | 4 | <1
Hyponatremia | 30 | 8 | 26 | 6
Increased GGT | 27 | 5 | 43 | 9
Hematology
Leukopenia | 35 | <1 | 31 | <1
Neutropenia | 31 | 2 | 17 | <1
Anemia [Based on laboratory abnormalities] | 31 | 4 | 71 | 17
Lymphopenia | 25 | 7 | 39 | 12
Thrombocytopenia | 25 | <1 | 27 | <1
ALP, alkaline phosphatase; ALT, alanine aminotransferase; AST, aspartate aminotransferase; GGT, gamma glutamyl transferase.
NCI CTCAE, Version 4.0

CABOSUN

The safety of CABOMETYX was evaluated in CABOSUN, a randomized, open-label trial in patients with advanced renal cell carcinoma, in which 78 patients received CABOMETYX 60 mg once daily and 72 patients received sunitinib 50 mg once daily (4 weeks on treatment followed by 2 weeks off), until disease progression or unacceptable toxicity [see Clinical Studies (14.1)]. The median duration of treatment was 6.5 months (range 0.2 – 28.7) for patients receiving CABOMETYX and 3.1 months (range 0.2 – 25.5) for patients receiving sunitinib.

Within 30 days of treatment, there were 4 deaths in patients treated with CABOMETYX and 6 deaths in patients treated with sunitinib. Of the 4 patients treated with CABOMETYX, 2 patients died due to gastrointestinal perforation, 1 patient had acute renal failure, and 1 patient died due to clinical deterioration. All Grade 3-4 adverse reactions were collected in the entire safety population. The most frequent Grade 3-4 adverse reactions (≥5%) in patients treated with CABOMETYX were hypertension, diarrhea, hyponatremia, hypophosphatemia, PPE, fatigue, increased ALT, decreased appetite, stomatitis, pain, hypotension, and syncope.

The median average daily dose was 50.3 mg for CABOMETYX and 44.7 mg for sunitinib (excluding scheduled sunitinib non-dosing days). The dose was reduced in 46% of patients receiving CABOMETYX and in 35% of patients receiving sunitinib. The dose was held in 73% of patients receiving CABOMETYX and in 71% of patients receiving sunitinib. Based on patient disposition, 21% of patients receiving CABOMETYX and 22% of patients receiving sunitinib discontinued due to an adverse reaction.

Table 7. Grade 3-4 Adverse Reactions Occurring in ≥ 1% Patients Who Received CABOMETYX in CABOSUN
Adverse Reaction | CABOMETYX (n = 78) | Sunitinib (n = 72)
Adverse Reaction | Grade 3-4 [NCI CTCAE Version 4.0] | Grade 3-4
Adverse Reaction | Percentage (%) of Patients
Patients with any Grade 3-4 Adverse Reaction | 68 | 65
Gastrointestinal
Diarrhea | 10 | 11
Stomatitis | 5 | 6
Nausea | 3 | 4
Vomiting | 1 | 3
Constipation | 1 | 0
General
Fatigue | 6 | 17
Pain | 5 | 0
Metabolism and Nutrition
Hyponatremia [Laboratory abnormalities are reported as adverse reactions and not based on shifts in laboratory values] | 9 | 8
Hypophosphatemia | 9 | 7
Decreased appetite | 5 | 1
Dehydration | 4 | 1
Hypocalcemia | 3 | 0
Hypomagnesemia | 3 | 0
Hypokalemia | 1 | 3
Skin and Subcutaneous Tissue
Palmar-plantar erythrodysesthesia | 8 | 4
Skin Ulcer | 3 | 0
Vascular
Hypertension [Includes the following term: hypertension] | 28 | 21
Hypotension | 5 | 1
Angiopathy | 1 | 1
Investigations
Increased ALT | 5 | 0
Weight decreased | 4 | 0
Increased AST | 3 | 3
Increased blood creatinine | 3 | 3
Lymphopenia | 1 | 6
Thrombocytopenia | 1 | 11
Nervous System
Syncope | 5 | 0
Respiratory, Thoracic, and Mediastinal
Dyspnea | 1 | 6
Dysphonia | 1 | 0
Blood and Lymphatic
Anemia | 1 | 3
Psychiatric
Depression | 4 | 0
Confusional state | 1 | 1
Infections
Lung Infection | 4 | 0
Musculoskelatal and Connective Tissue
Back pain | 4 | 0
Bone pain | 3 | 1
Pain in extremity | 3 | 0
Arthralgia | 1 | 0
Renal and Urinary
Renal failure acute | 4 | 1
Proteinuria | 3 | 1
ALT, alanine aminotransferase; AST, aspartate aminotransferase

CHECKMATE-9ER

The safety of CABOMETYX with nivolumab was evaluated in CHECKMATE-9ER, a randomized, open-label study in patients with previously untreated advanced RCC [see Clinical Studies (14.1)]. Patients received CABOMETYX 40 mg orally once daily with nivolumab 240 mg over 30 minutes every 2 weeks (n=320) or sunitinib 50 mg daily, administered orally for 4 weeks on treatment followed by 2 weeks off (n=320) [see Clinical Studies (14.1)]. CABOMETYX could be interrupted or reduced to 20 mg daily or 20 mg every other day. The median duration of treatment was 14 months (range: 0.2 to 27 months) in CABOMETYX and nivolumab-treated patients. In this trial, 82% of patients in the CABOMETYX and nivolumab arm were exposed to treatment for >6 months and 60% of patients were exposed to treatment for >1 year.

Serious adverse reactions occurred in 48% of patients receiving CABOMETYX and nivolumab. The most frequent (≥2%) serious adverse reactions were diarrhea, pneumonia, pneumonitis, pulmonary embolism, urinary tract infection, and hyponatremia. Fatal intestinal perforations occurred in 3 (0.9%) patients.

Adverse reactions leading to discontinuation of either CABOMETYX or nivolumab occurred in 20% of patients: 8% CABOMETYX only, 7% nivolumab only, and 6% both drugs due to the same adverse reaction at the same time. Adverse reactions leading to dose interruption or reduction of either CABOMETYX or nivolumab occurred in 83% of patients: 46% CABOMETYX only, 3% nivolumab only, and 21% both drugs due to the same adverse reaction at the same time, and 6% both drugs sequentially.

The most common adverse reactions reported in ≥20% of patients treated with CABOMETYX and nivolumab were diarrhea, fatigue, hepatotoxicity, PPE, stomatitis, rash, hypertension, hypothyroidism, musculoskeletal pain, decreased appetite, nausea, dysgeusia, abdominal pain, cough, and upper respiratory tract infection.

Table 8. Adverse Reactions in >15% of Patients Receiving CABOMETYX and Nivolumab - CHECKMATE-9ER
Adverse Reaction | CABOMETYX and Nivolumab (n=320) |  | Sunitinib (n=320)
Adverse Reaction | Grades 1-4 | Grades 3-4 | Grades 1-4 | Grades 3-4
 | Percentage (%) of Patients
Gastrointestinal
Diarrhea | 64 | 7 | 47 | 4.4
Nausea | 27 | 0.6 | 31 | 0.3
Abdominal pain [Includes abdominal discomfort, abdominal pain lower, abdominal pain upper.] | 22 | 1.9 | 15 | 0.3
Vomiting | 17 | 1.9 | 21 | 0.3
Dyspepsia [Includes gastroesophageal reflux disease.] | 15 | 0 | 22 | 0.3
General
Fatigue [Includes asthenia.] | 51 | 8 | 50 | 8
Hepatobiliary
Hepatotoxicity [Includes hepatotoxicity, ALT increased, AST increased, blood alkaline phosphatase increased, gamma-glutamyl transferase increased, autoimmune hepatitis, blood bilirubin increased, drug induced liver injury, hepatic enzyme increased, hepatitis, hyperbilirubinemia, liver function test increased, liver function test abnormal, transaminases increased, hepatic failure.] | 44 | 11 | 26 | 5
Skin and Subcutaneous Tissue
Palmar-plantar erythrodysesthesia | 40 | 8 | 41 | 8
Stomatitis [Includes mucosal inflammation, aphthous ulcer, mouth ulceration.] | 37 | 3.4 | 46 | 4.4
Rash [Includes dermatitis, dermatitis acneiform, dermatitis bullous, exfoliative rash, rash erythematous, rash follicular, rash macular, rash maculo-papular, rash papular, rash pruritic.] | 36 | 3.1 | 14 | 0
Pruritus | 19 | 0.3 | 4.4 | 0
Vascular
Hypertension [Includes blood pressure increased, blood pressure systolic increased.] | 36 | 13 | 39 | 14
Endocrine
Hypothyroidism [Includes primary hypothyroidism.] | 34 | 0.3 | 30 | 0.3
Musculoskeletal and Connective Tissue
Musculoskeletal pain [Includes back pain, bone pain, musculoskeletal chest pain, musculoskeletal discomfort, myalgia, neck pain, pain in extremity, spinal pain.] | 33 | 3.8 | 29 | 3.1
Arthralgia | 18 | 0.3 | 9 | 0.3
Metabolism and Nutrition
Decreased appetite | 28 | 1.9 | 20 | 1.3
Nervous System Disorders
Dysgeusia | 24 | 0 | 22 | 0
Headache | 16 | 0 | 12 | 0.6
Respiratory, Thoracic and Mediastinal
Cough [Includes productive cough.] | 20 | 0.3 | 17 | 0
Dysphonia | 17 | 0.3 | 3.4 | 0
Infections and Infestations
Upper respiratory tract infection [Includes nasopharyngitis, pharyngitis, rhinitis.] | 20 | 0.3 | 8 | 0.3
Toxicity was graded per NCI CTCAE v4.

Table 9. Laboratory Values Worsening from Baseline [Each test incidence is based on the number of patients who had both baseline and at least one on-study laboratory measurement available: CABOMETYX and nivolumab group (range: 170 to 317 patients) and sunitinib group (range: 173 to 311 patients).] Occurring in >20% of Patients Receiving CABOMETYX and Nivolumab - CHECKMATE-9ER
Laboratory Abnormality | CABOMETYX and Nivolumab |  | Sunitinib
Laboratory Abnormality | Grades 1-4 | Grades 3-4 | Grades 1-4 | Grades 3-4
 | Percentage (%) of Patients
Chemistry
Increased ALT | 79 | 9.8 | 39 | 3.5
Increased AST | 77 | 7.9 | 57 | 2.6
Hypophosphatemia | 69 | 28 | 48 | 10
Hypocalcemia | 54 | 1.9 | 24 | 0.6
Hypomagnesemia | 47 | 1.3 | 25 | 0.3
Hyperglycemia | 44 | 3.5 | 44 | 1.7
Hyponatremia | 43 | 11 | 36 | 12
Increased lipase | 41 | 14 | 38 | 13
Increased amylase | 41 | 10 | 28 | 6
Increased alkaline phosphatase | 41 | 2.8 | 37 | 1.6
Increased creatinine | 39 | 1.3 | 42 | 0.6
Hyperkalemia | 35 | 4.7 | 27 | 1
Hypoglycemia | 26 | 0.8 | 14 | 0.4
Hematology
Lymphopenia | 42 | 6.6 | 45 | 10
Thrombocytopenia | 41 | 0.3 | 70 | 9.7
Anemia | 37 | 2.5 | 61 | 4.8
Leukopenia | 37 | 0.3 | 66 | 5.1
Neutropenia | 35 | 3.2 | 67 | 12

Hepatocellular Carcinoma

The safety of CABOMETYX was evaluated in CELESTIAL, a randomized, double-blind, placebo-controlled trial in which 704 patients with advanced hepatocellular carcinoma were randomized to receive CABOMETYX 60 mg orally once daily (n=467) or placebo (n=237) until disease progression or unacceptable toxicity [see Clinical Studies (14.2)]. The median duration of treatment was 3.8 months (range 0.1 – 37.3) for patients receiving CABOMETYX and 2.0 months (range 0.0 – 27.2) for patients receiving placebo. The population exposed to CABOMETYX was 81% male, 56% White, and had a median age of 64 years.

Adverse reactions occurring in ≥25% of CABOMETYX-treated patients, in order of decreasing frequency were: diarrhea, decreased appetite, PPE, fatigue, nausea, hypertension, and vomiting. Grade 3-4 adverse reactions which occurred in ≥5% of patients were PPE, hypertension, fatigue, diarrhea, asthenia, and decreased appetite. There were 6 adverse reactions leading to death in patients receiving CABOMETYX (hepatic failure, hepatorenal syndrome, esophagobronchial fistula, portal vein thrombosis, pulmonary embolism, upper gastrointestinal hemorrhage).

The median average daily dose was 35.8 mg for CABOMETYX. The dose was reduced in 62% of patients receiving CABOMETYX; 33% of patients required a reduction to 20 mg daily. The most frequent adverse reactions or laboratory abnormalities leading to dose reduction of CABOMETYX were: PPE, diarrhea, fatigue, hypertension, and increased AST. Adverse reactions leading to dose interruption occurred in 84% patients receiving CABOMETYX. Adverse reactions leading to permanent discontinuation of CABOMETYX occurred in 16% of patients. The most frequent adverse reactions leading to permanent discontinuation of CABOMETYX were PPE (2%), fatigue (2%), decreased appetite (1%), diarrhea (1%), and nausea (1%).

Table 10. Adverse Reactions Occurring in ≥ 5% of CABOMETYX-Treated Patients in CELESTIAL [Includes terms with a between-arm difference of ≥ 5% (all grades) or ≥ 2% (Grade 3-4)]
Adverse Reaction | CABOMETYX (n=467) |  | Placebo (n=237)
Adverse Reaction | All Grades [NCI CTCAE Version 4.0] | Grade 3-4 | All Grades | Grade 3-4
 | Percentage (%) of Patients
Gastrointestinal
Diarrhea | 54 | 10 | 19 | 2
Nausea | 31 | 2 | 18 | 2
Vomiting | 26 | <1 | 12 | 3
Stomatitis | 13 | 2 | 2 | 0
Dyspepsia | 10 | 0 | 3 | 0
General
Fatigue | 45 | 10 | 30 | 4
Asthenia | 22 | 7 | 8 | 2
Mucosal inflammation | 14 | 2 | 2 | <1
Metabolism and Nutrition
Decreased appetite | 48 | 6 | 18 | <1
Skin and Subcutaneous Tissue
Palmar-plantar erythrodysesthesia | 46 | 17 | 5 | 0
Rash [Includes the following terms: rash, rash erythematous, rash generalized, rash macular, rash maculo- papular, rash papular, rash pruritic, rash pustular, rash vesicular, dermatitis, dermatitis acneiform, dermatitis contact, dermatitis diaper, dermatitis exfoliative, dermatitis infected] | 21 | 2 | 9 | <1
Vascular
Hypertension [Includes the following terms: hypertension, blood pressure diastolic increased, blood pressure increased] | 30 | 16 | 6 | 2
Investigations
Weight decreased | 17 | 1 | 6 | 0
Nervous System
Dysgeusia | 12 | 0 | 2 | 0
Endocrine
Hypothyroidism | 8 | <1 | <1 | 0
Respiratory, Thoracic, and Mediastinal
Dysphonia | 19 | 1 | 2 | 0
Dyspnea | 12 | 3 | 10 | <1
Musculoskeletal and Connective Tissue
Pain in extremity | 9 | <1 | 4 | 1
Muscle spasms | 8 | <1 | 2 | 0

Table 11. Laboratory Abnormalities Occurring in ≥5% of CABOMETYX-Treated Patients in CELESTIAL [Includes laboratory abnormalities with a between-arm difference of ≥5% (all grades) or ≥2% (Grade 3-4)]
Laboratory Abnormality | CABOMETYX (n=467) |  | Placebo (n=237)
Laboratory Abnormality | All Grades | Grade 3-4 | All Grades | Grade 3-4
 | Percentage (%) of Patients
Chemistry
Increased LDH | 84 | 9 | 29 | 2
Increased ALT | 73 | 12 | 37 | 6
Increased AST | 73 | 24 | 46 | 19
Hypoalbuminemia | 51 | 1 | 32 | 1
Increased ALP | 43 | 8 | 38 | 6
Hypophosphatemia | 25 | 9 | 8 | 4
Hypokalemia | 23 | 6 | 6 | 1
Hypomagnesemia | 22 | 3 | 3 | 0
Increased amylase | 16 | 2 | 9 | 2
Hypocalcemia | 8 | 2 | 0 | 0
Hematology
Decreased platelets | 54 | 10 | 16 | 1
Neutropenia | 43 | 7 | 8 | 1
Increased hemoglobin | 8 | 0 | 1 | 0
ALP, alkaline phosphatase; ALT, alanine aminotransferase; AST, aspartate aminotransferase; LDH, blood lactate dehydrogenase

Differentiated Thyroid Cancer

The safety of CABOMETYX was evaluated in COSMIC-311, a randomized, double-blind, placebo-controlled trial in which 187 patients with advanced differentiated thyroid cancer were randomized to receive CABOMETYX 60 mg orally once daily (n=125) or placebo (n=62) with supportive care until disease progression or unacceptable toxicity [see Clinical Studies (14.3)]. At the time of the primary efficacy analysis, the median duration of treatment was 4.4 months (range 0.0 – 15.7) for patients receiving CABOMETYX and 2.3 months (range 0.3 – 11.6) for patients receiving placebo. The median age was 66 years (range 32 to 85 years), 55% were female, 70% were White, 18% were Asian, 2% were Black, 2% were American Indian or Alaska Native, and 63% received prior lenvatinib.

Adverse reactions occurring in ≥25% of CABOMETYX-treated patients, in order of decreasing frequency were: diarrhea, PPE, fatigue, hypertension, and stomatitis. Grade 3-4 adverse reactions which occurred in ≥5% of patients were PPE, hypertension, fatigue, diarrhea, and stomatitis. Serious adverse reactions occurred in 34% of patients who received CABOMETYX. Serious adverse reactions in ≥2% included diarrhea, pleural effusion, pulmonary embolism and dyspnea. Fatal adverse reactions occurred in 1.6% of patients in the CABOMETYX arm, including arterial hemorrhage (0.8%) and pulmonary embolism (0.8%).

The median average daily dose was 42.0 mg for CABOMETYX. The dose was reduced in 56% of patients receiving CABOMETYX; 22% of patients required a second dose reduction. The most frequent adverse reactions (≥5%) leading to dose reduction of CABOMETYX were PPE, diarrhea, fatigue, proteinuria, and decreased appetite. Dose interruptions occurred in 72% patients receiving CABOMETYX. Adverse reactions requiring dosage interruption in ≥5% of patients were PPE, diarrhea, dyspnea, hypertension, decreased appetite and proteinuria. Adverse reactions leading to permanent discontinuation of CABOMETYX occurred in 5% of patients.

Table 12. Adverse Reactions Occurring in ≥5% of CABOMETYX-Treated Patients in COSMIC-311 [Includes terms that are more frequent in the CABOMETYX arm and have a between-arm difference of 2 ≥5% (all grades) or ≥2% (Grade 3-4)]
Adverse Reaction | CABOMETYX (N=125) |  | Placebo (N=62)
Adverse Reaction | All Grades [NCI CTCAE Version 5.0] | Grade 3-4 | All Grades | Grade 3-4
 | Percentage of Patients
Gastrointestinal
Diarrhea | 51 | 7 | 3 | 0
Nausea | 24 | 3 | 2 | 0
Vomiting | 14 | 1 | 8 | 0
Stomatitis [Includes the following terms: mucosal inflammation, stomatitis] | 26 | 5 | 3 | 0
Dry mouth | 10 | 1 | 2 | 0
General
Fatigue [Includes the following terms: fatigue, asthenia] | 42 | 10 | 23 | 0
Metabolism and Nutrition
Decreased appetite | 23 | 3 | 16 | 0
Skin and Subcutaneous Tissue
Palmar-plantar erythrodysesthesia | 46 | 10 | 0 | 0
Vascular
Hypertension [Includes the following terms: hypertension, blood pressure increased, hypertensive crisis] | 30 | 10 | 5 | 3
Investigations
Weight decreased | 18 | 1 | 5 | 0
Nervous System
Dysgeusia | 10 | 0 | 0 | 0
Headache | 10 | 2 | 2 | 0
Respiratory, Thoracic, and Mediastinal
Dysphonia | 10 | 0 | 2 | 0
Pulmonary embolism | 5 | 2 | 0 | 0
Renal and Urinary
Proteinuria | 15 | 1 | 3 | 0

Table 13. Laboratory Abnormalities Occurring in ≥10% of CABOMETYX-Treated Patients in COSMIC-311 [Includes laboratory abnormalities that are more frequent in the CABOMETYX arm and have a between-arm difference of ≥5% (all grades) or ≥2% (Grade 3-4)]
Laboratory Abnormality | CABOMETYX (N=125) |  | Placebo (N=62)
Laboratory Abnormality | All Grades | Grade 3 or 4 | All Grades | Grade 3 or 4
 | Percentage of Patients
Chemistry
LDH increased [Sponsor-defined grades for LDH were as follows: Grade 1 (> ULN to ≤2 × ULN), Grade 2 (>2 × ULN to ≤3 × ULN), Grade 3 (>3 × ULN).] | 90 | 10 | 32 | 3
AST increased | 77 | 1 | 18 | 0
ALT increased | 66 | 2 | 11 | 0
Hypocalcemia | 36 | 9 | 10 | 2
ALP increased | 34 | 0 | 15 | 0
GGT increased | 26 | 2 | 21 | 2
Hypomagnesemia | 25 | 2 | 5 | 0
Hypoalbuminemia | 19 | 1 | 7 | 0
Hypokalemia | 18 | 1 | 3 | 0
Hyponatremia | 15 | 0 | 10 | 2
Hyperbilirubinemia | 12 | 0 | 5 | 0
Hematology
Leukocytes decreased | 38 | 2 | 7 | 2
Neutrophils decreased | 31 | 2 | 5 | 2
Platelets decreased | 26 | 0 | 5 | 0
ALP, alkaline phosphatase; ALT, alanine aminotransferase; AST, aspartate aminotransferase; GGT, gamma glutamyl transferase; LDH, blood lactate dehydrogenase

Neuroendocrine Tumors

Pancreatic Neuroendocrine Tumors (pNET)

The safety of CABOMETYX was evaluated in adult patients with unresectable, locally advanced or metastatic, well-differentiated neuroendocrine tumors in the CABINET trial [see Clinical Studies (14.4)]. Patients received CABOMETYX 60 mg (n=63) or placebo orally (n=31) once daily until disease progression or unacceptable toxicity. Patients with pNET were required to have disease progression after prior treatment with at least one FDA approved therapy (everolimus, sunitinib or lutetium Lu 177 dotatate), other than somatostatin analogs. The median duration of treatment was 8.3 months (range: 0.1 to 37.8) for patients receiving CABOMETYX and 2.9 months (range: 0.1 to 11.2) for patients receiving placebo.

The median age of patients who received CABOMETYX was 60 years (range: 29 to 79), 57% were male, 86% were White, 6% were Asian, 3.2% were Black, 1.6% were American Indian or Alaska Native, 1.6% were Native Hawaiian or Other Pacific Islanders, and 3.2% were Hispanic or Latino.

Serious adverse reactions occurred in 46% of patients who received CABOMETYX. Serious adverse reactions in ≥2% of patients included thromboembolic events (10%), vomiting (6%), sepsis (4.8%), nausea (4.8%), hypoxia (4.8%), hemorrhage (3.2%), abdominal pain (3.2%), musculoskeletal pain (3.2%), blood bilirubin increased (3.2%), fatigue (3.2%), hyperkalemia (3.2%), and hypertension (3.2%).

Permanent discontinuation of CABOMETYX due to an adverse reaction occurred in 19% of patients. Adverse reactions which resulted in permanent discontinuation of CABOMETYX included thromboembolic events, acute kidney injury, rash, dyspnea, fistulas, hemorrhage, cardiac arrest, musculoskeletal pain, COVID-19 infection, Cushing’s syndrome, pneumonia, proteinuria, and myocardial infarction.

The median average daily dose was 41.4 mg for CABOMETYX. Dosage interruptions of CABOMETYX due to an adverse reaction occurred in 83% of patients. Adverse reactions which required dosage interruption in ≥5% of patients included rash, diarrhea, fatigue, thromboembolic events, nausea, hypertension, increased ALT, blood bilirubin increased, musculoskeletal pain, stomatitis, vomiting, and increased AST.

Dose reductions of CABOMETYX due to an adverse reaction occurred in 49% of patients. Adverse reactions which required dose reductions in ≥5% of patients included rash, fatigue, hypertension, and stomatitis.

The most common adverse reactions occurring in ≥20% of CABOMETYX-treated patients were fatigue, increased AST, increased ALT, hypertension, diarrhea, rash, stomatitis, musculoskeletal pain, hyperglycemia, nausea, platelet count decreased, dysgeusia, neutrophil count decreased, abdominal pain, decreased appetite, hemoglobin decreased, dizziness, hypophosphatemia, hypothyroidism, vomiting, increased ALP, and lymphocyte count decreased.

Table 14 summarizes the adverse reactions in patients with pNET in CABINET.

Table 14. Adverse Reactions (≥15%) in Patients with pNET Who Received CABOMETYX in CABINET
Adverse Reaction | CABOMETYX (N=63) |  | Placebo (N=31)
Adverse Reaction | All Grades [NCI CTCAE Version 5.0] | Grade 3 or 4 | All Grades | Grade 3 or 4
 | Percentage (%) of Patients
General
Fatigue [Includes fatigue, asthenia] | 79 | 14 | 61 | 6
Vascular
Hypertension [Includes hypertension, blood pressure increased, blood pressure systolic increased, systolic hypertension] | 67 | 25 | 55 | 16
Thromboembolic events [Includes thromboembolic event, pulmonary embolism, embolism, deep vein thrombosis, vena cava thrombosis, embolism venous, embolism arterial] | 19 | 11 | 3.2 | 0
Gastrointestinal
Diarrhea [Includes diarrhea, colitis] | 63 | 6 | 23 | 0
Stomatitis [Includes stomatitis, aphthous ulcer, mucosal inflammation, cheilitis, glossitis] | 49 | 6 | 10 | 0
Nausea | 37 | 8 | 32 | 3.2
Abdominal pain [Includes abdominal pain, abdominal pain lower, abdominal pain upper, gastrointestinal pain, abdominal discomfort, hepatic pain] | 25 | 3.2 | 16 | 6
Vomiting | 25 | 6 | 16 | 0
Dyspepsia [Includes dyspepsia, gastroesophageal reflux disease] | 16 | 0 | 6 | 0
Skin and Subcutaneous Tissue
Rash [Includes rash, palmar-plantar erythrodysesthesia syndrome, dermatitis acneiform, skin exfoliation, erythema multiforme, rash macular, rash maculo-papular, rash pustular, dermatitis, dermatitis bullous, dermatitis contact, erythema, dermatitis psoriasiform] | 57 | 11 | 23 | 0
Musculoskeletal and Connective Tissue Disorders
Musculoskeletal pain [Includes musculoskeletal pain, non-cardiac chest pain, back pain, arthralgia, pain in extremity, myalgia, bone pain, arthritis, neck pain, musculoskeletal chest pain, musculoskeletal stiffness, chest discomfort] | 41 | 1.6 | 19 | 0
Nervous System
Dysgeusia [Includes dysgeusia, taste disorder, ageusia, anosmia] | 30 | 0 | 6 | 0
Dizziness [Includes dizziness, vertigo] | 25 | 0 | 3.2 | 0
Endocrine disorders
Hypothyroidism [Includes hypothyroidism, blood thyroid stimulating hormone increased] | 25 | 0 | 3.2 | 0
Metabolism and Nutrition
Decreased appetite | 25 | 3.2 | 19 | 0
Investigations
Weight decreased | 19 | 3.2 | 10 | 0
Respiratory, Thoracic, and Mediastinal
Dyspnea [Includes dyspnea, dyspnea exertional] | 16 | 0 | 3.2 | 0

Clinically relevant adverse reactions in <15% of patients who received CABOMETYX included peripheral neuropathy, hemorrhage, cardiac arrhythmia, hypotension, alopecia, and hair color changes.

Table 15 summarizes the laboratory abnormalities in patients with pNET in CABINET.

Table 15: Select Laboratory Abnormalities (≥10%) Reported as Adverse Reactions in Patients with pNET Who Received CABOMETYX in CABINET
Laboratory Abnormality | CABOMETYX (N=63) |  | Placebo (N=31)
Laboratory Abnormality | All Grades [NCI CTCAE Version 5.0] (%) | Grade 3 or 4 (%) | All Grades (%) | Grade 3 or 4 (%)
Chemistry
Increased AST | 76 | 1.6 | 48 | 0
Increased ALT | 75 | 1.6 | 39 | 3.2
Hyperglycemia [Includes hyperglycemia, blood glucose increased] | 37 | 3.2 | 48 | 3.2
Hypophosphatemia [Includes hypophosphatemia, blood phosphorus decreased] | 25 | 0 | 6 | 0
Increased ALP [Includes blood alkaline phosphatase, blood alkaline phosphatase increased] | 22 | 3.2 | 23 | 0
Hypocalcemia [Includes hypocalcemia, blood calcium decreased, adjusted calcium decreased] | 17 | 0 | 3.2 | 0
Hyponatremia [Includes hyponatremia, blood sodium decreased] | 16 | 1.6 | 16 | 0
Blood bilirubin increased [Includes blood bilirubin increased, hyperbilirubinemia] | 14 | 4.8 | 6 | 3.2
Hyperkalemia [Includes hyperkalemia, blood potassium increased] | 14 | 1.6 | 10 | 0
Hypoalbuminemia [Includes hypoalbuminemia, blood albumin decreased] | 14 | 0 | 10 | 0
Hypoglycemia [Includes hypoglycemia, blood glucose decreased] | 11 | 0 | 6 | 0
Hypomagnesemia [Includes hypomagnesemia, blood magnesium decreased] | 11 | 0 | 6 | 0
Hypokalemia [Includes hypokalemia, blood potassium decreased] | 10 | 1.6 | 3.2 | 0
Hematology
Platelet count decreased [Includes platelet count decreased, thrombocytopenia] | 37 | 0 | 19 | 0
Neutrophil count decreased [Includes neutrophil count decreased, neutropenia] | 27 | 1.6 | 6 | 0
Hemoglobin decreased [Includes hemoglobin decreased, anemia] | 25 | 1.6 | 32 | 0
Lymphocyte count decreased [Includes lymphocyte count decreased, lymphopenia] | 22 | 8 | 16 | 0
White blood cell count decreased [Includes white blood cell count decreased, leukopenia] | 19 | 1.6 | 3.2 | 0

Extra-Pancreatic Neuroendocrine Tumors (epNET)

The safety of CABOMETYX was evaluated in adult patients with unresectable, locally advanced or metastatic, well-differentiated neuroendocrine tumors in the CABINET trial [see Clinical Studies (14.4)]. Patients received CABOMETYX 60 mg (n=132) or placebo (n=67) orally once daily until disease progression or unacceptable toxicity. Patients with epNET were required to have disease progression after prior treatment with at least one FDA approved therapy (everolimus or lutetium Lu 177 dotatate), other than somatostatin analogs. The median duration of treatment was 5.4 months (range 0.1 to 32.4) for patients receiving CABOMETYX and 2.8 months (range 0.5 to 22.8) for patients receiving placebo.

The median age was 66 years (range 28 to 86), 55% were female, 86% were White, 7% were Black, 2.3% were Asian, 5% had unknown race or race not reported, and 6% were Hispanic or Latino.

Serious adverse reactions occurred in 44% of patients who received CABOMETYX. Serious adverse reactions in ≥2% included hypertension (6%), abdominal pain (5%), musculoskeletal pain (5%), diarrhea (3.0%), vomiting (3.0%), blood bilirubin increased (3.0%), thromboembolic events (3.0%), nausea (2.3%), hemoglobin decreased (2.3%), muscular weakness (2.3%), fatigue (2.3%), sepsis (2.3%), and syncope (2.3%). Fatal adverse reactions occurred in 4.5% of patients who received CABOMETYX, including hepatic failure, multi-organ dysfunction, gastrointestinal hemorrhage, cardiac arrest, ruptured ascending aortic aneurysm, and sudden death not otherwise specified, occurring in one patient each.

Permanent discontinuation of CABOMETYX due to an adverse reaction occurred in 28% of patients receiving CABOMETYX. Adverse reactions which resulted in permanent discontinuation of CABOMETYX included diarrhea, fatigue, increased AST, increased ALT, blood bilirubin increased, rash, thromboembolic events, hypertension, increased ALP, nausea, and stomatitis.

The median average daily dose was 42.9 mg for CABOMETYX. Dosage interruptions of CABOMETYX due to an adverse reaction occurred in 81% of patients. Adverse reactions which required dosage interruption in ≥5% of patients included diarrhea, fatigue, rash, hypertension, nausea, stomatitis, abdominal pain, increased AST, vomiting, and musculoskeletal pain.

Dose reductions of CABOMETYX due to an adverse reaction occurred in 38% of patients. Adverse reactions which required dose reductions in ≥5% of patients included rash, fatigue, diarrhea, and hypertension.

The most common adverse reactions occurring in ≥20% of CABOMETYX-treated patients were fatigue, increased AST, diarrhea, hypertension, increased ALT, platelet count decreased, rash, stomatitis, nausea, white blood cell count decreased, neutrophil count decreased, musculoskeletal pain, dysgeusia, hypothyroidism, decreased appetite, hemoglobin decreased, hyperglycemia, abdominal pain, increased ALP, lymphocyte count decreased, weight decreased, blood creatinine increased, hypoalbuminemia, blood bilirubin increased, hypocalcemia, hypokalemia, and hypomagnesemia.

Table 16 summarizes the adverse reactions in patients with epNET in CABINET.

Table 16. Adverse Reactions (≥15%) in Patients with epNET Who Received CABOMETYX in CABINET
Adverse Reaction | CABOMETYX (N=132) |  | Placebo (N=67)
Adverse Reaction | All Grades [NCI CTCAE Version 5.0] | Grade 3-4 | All Grades | Grade 3-4
 | Percentage (%) of Patients
General
Fatigue [Includes fatigue, asthenia] | 73 | 14 | 58 | 9
Edema [Includes edema, edema peripheral, generalized edema, localized edema, periorbital edema, face edema, eye edema] | 16 | 1.5 | 10 | 0
Gastrointestinal
Diarrhea [Includes diarrhea, colitis] | 65 | 11 | 42 | 4.5
Stomatitis [Includes stomatitis, aphthous ulcer, mucosal inflammation, cheilitis, glossitis] | 40 | 3.8 | 10 | 0
Nausea | 39 | 2.3 | 21 | 0
Abdominal pain [Includes abdominal pain, abdominal pain lower, abdominal pain upper, gastrointestinal pain, abdominal discomfort, hepatic pain] | 29 | 9 | 43 | 8
Vomiting | 17 | 2.3 | 10 | 1.5
Vascular
Hypertension [Includes hypertension, blood pressure increased, blood pressure systolic increased, systolic hypertension] | 64 | 27 | 37 | 6
Skin and Subcutaneous Tissue
Rash [Includes rash, palmar-plantar erythrodysesthesia syndrome, dermatitis acneiform, skin exfoliation, rash macular, rash pustular, dermatitis bullous, dermatitis, erythema multiforme, rash maculo-papular, dermatitis contact, erythema, dermatitis psoriasiform] | 50 | 3.0 | 10 | 0
Musculoskeletal and Connective Tissue Disorders
Musculoskeletal pain [Includes musculoskeletal pain, non-cardiac chest pain, back pain, arthralgia, pain in extremity, myalgia, bone pain, arthritis, neck pain, musculoskeletal chest pain, musculoskeletal stiffness, chest discomfort] | 36 | 8 | 33 | 1.5
Endocrine System
Hypothyroidism [Includes hypothyroidism, blood thyroid stimulating hormone increased] | 34 | 0 | 4.5 | 0
Metabolism and Nutrition
Decreased appetite | 33 | 1.5 | 15 | 1.5
Nervous System
Dysgeusia [Includes dysgeusia, taste disorder, ageusia, anosmia] | 35 | 0 | 1.5 | 0
Dizziness [Includes dizziness, vertigo] | 17 | 0 | 6 | 0
Investigations
Weight decreased | 27 | 4.5 | 8 | 0
Respiratory, Thoracic, and Mediastinal
Cough [Includes cough, upper-airway cough syndrome, productive cough] | 17 | 0 | 10 | 0

Clinically relevant adverse reactions in <15% of patients who received CABOMETYX included cardiac arrhythmia, hemorrhage, thromboembolic events, kidney injury, proteinuria, hypotension, peripheral neuropathy, reversible posterior leukoencephalopathy syndrome, alopecia, hair color changes, and cardiac failure.

Table 17 summarizes the laboratory abnormalities in patients with epNET in CABINET.

Table 17: Select Laboratory Abnormalities (≥10%) Reported as Adverse Reactions in Patients with epNET Who Received CABOMETYX in CABINET
Laboratory Abnormality | CABOMETYX (N=132) |  | Placebo (N=67)
Laboratory Abnormality | All Grades [NCI CTCAE Version 5.0] (%) | Grade 3 or 4 (%) | All Grades (%) | Grade 3 or 4 (%)
Chemistry
Increased AST | 70 | 3.8 | 21 | 1.5
Increased ALT | 63 | 0.8 | 18 | 1.5
Hyperglycemia [Includes hyperglycemia, blood glucose increased] | 30 | 0.8 | 39 | 1.5
Increased ALP [Includes blood alkaline phosphatase, blood alkaline phosphatase increased] | 29 | 4.5 | 30 | 6
Blood creatinine increased | 23 | 0 | 12 | 1.5
Blood bilirubin increased [Includes blood bilirubin increased, hyperbilirubinemia] | 20 | 3 | 10 | 6
Hypoalbuminemia [Includes hypoalbuminemia, blood albumin decreased] | 20 | 0.8 | 9 | 0
Hypocalcemia [Includes hypocalcemia, blood calcium decreased, adjusted calcium decreased] | 20 | 0 | 4.5 | 0
Hypokalemia [Includes hypokalemia, blood potassium decreased] | 20 | 2.3 | 10 | 1.5
Hypomagnesemia [Includes hypomagnesemia, blood magnesium decreased] | 20 | 0.8 | 4.5 | 0
Hypophosphatemia [Includes hypophosphatemia, blood phosphorus decreased] | 19 | 0.8 | 4.5 | 0
Hyponatremia [Includes hyponatremia, blood sodium decreased] | 16 | 2.3 | 7 | 1.5
Hematology
Platelet count decreased [Includes platelet count decreased, thrombocytopenia] | 55 | 1.5 | 13 | 1.5
White blood cell count deceased [Includes white blood cell count decreased, leukopenia] | 37 | 3 | 4.5 | 0
Neutrophil count decreased [Includes neutrophil count decreased, neutropenia] | 36 | 3 | 6 | 0
Hemoglobin decreased [Includes hemoglobin decreased, anemia] | 30 | 2.3 | 19 | 0
Lymphocyte count decreased [Includes lymphocyte count decreased, lymphopenia] | 28 | 9 | 18 | 1.5

6.2 Postmarketing Experience

The following adverse reactions have been identified during post-approval use of CABOMETYX. Because these reactions are reported voluntarily from a population of uncertain size, it is not always possible to reliably estimate their frequency or establish a causal relationship to drug exposure.

Vascular Disorders: Arterial (including aortic) aneurysms, dissections, and rupture

7 DRUG INTERACTIONS

7.1 Effects of Other Drugs on CABOMETYX

Strong CYP3A4 Inhibitors

Coadministration of a cabozantinib capsule formulation with a strong CYP3A4 inhibitor increased the exposure of cabozantinib, which may increase the risk of exposure-related adverse reactions [see Clinical Pharmacology (12.3)]. Avoid coadministration of CABOMETYX with strong CYP3A4 inhibitors. Reduce the dosage of CABOMETYX if coadministration with strong CYP3A4 inhibitors cannot be avoided [see Dosage and Administration (2.4)]. Avoid grapefruit or grapefruit juice which may also increase exposure of cabozantinib.

Strong or Moderate CYP3A Inducers

Coadministration of a cabozantinib capsule formulation with a strong CYP3A4 inducer decreased the exposure of cabozantinib, which may reduce efficacy [see Clinical Pharmacology (12.3)]. Avoid coadministration of CABOMETYX with strong or moderate CYP3A4 inducers. Increase the dosage of CABOMETYX if coadministration with strong or moderate CYP3A4 inducers cannot be avoided [see Dosage and Administration (2.5)]. Avoid St. John’s wort which may also decrease exposure of cabozantinib.

8 USE IN SPECIFIC POPULATIONS

8.1 Pregnancy

Risk Summary

Based on findings from animal studies and its mechanism of action [see Clinical Pharmacology (12.1)], CABOMETYX can cause fetal harm when administered to a pregnant woman. There are no available data in pregnant women to inform the drug-associated risk. In animal developmental and reproductive toxicology studies administration of cabozantinib to pregnant rats and rabbits during organogenesis resulted in embryofetal lethality and structural anomalies at exposures that were below those occurring clinically at the recommended dose (see Data). Advise pregnant women of the potential risk to a fetus.

In the U.S. general population, the estimated background risk of major birth defects and miscarriage in clinically recognized pregnancies is 2-4% and 15-20%, respectively.

Data

Animal Data

In an embryo-fetal development study in pregnant rats, daily oral administration of cabozantinib throughout organogenesis caused increased embryo-fetal lethality compared to controls at a dose of 0.03 mg/kg (approximately 0.12-fold of human area under the curve [AUC] at the recommended dose). Findings included delayed ossification and skeletal variations at a dose of 0.01 mg/kg/day (approximately 0.04-fold of human AUC at the recommended dose).

In pregnant rabbits, daily oral administration of cabozantinib throughout organogenesis resulted in findings of visceral malformations and variations including reduced spleen size and missing lung lobe at 3 mg/kg (approximately 1.1-fold of the human AUC at the recommended dose).

In a pre- and postnatal study in rats, cabozantinib was administered orally from gestation day 10 through postnatal day 20. Cabozantinib did not produce adverse maternal toxicity or affect pregnancy, parturition or lactation of female rats, and did not affect the survival, growth or postnatal development of the offspring at doses up to 0.3 mg/kg/day (0.05-fold of the maximum recommended clinical dose).

8.2 Lactation

Risk Summary

There is no information regarding the presence of cabozantinib or its metabolites in human milk, or their effects on the breastfed child or milk production. Because of the potential for serious adverse reactions in breastfed children, advise women not to breastfeed during treatment with CABOMETYX and for 4 months after the final dose.

8.3 Females and Males of Reproductive Potential

Pregnancy Testing

Verify the pregnancy status of females of reproductive potential prior to initiating CABOMETYX [see Use in Specific Populations (8.1)].

Contraception

CABOMETYX can cause fetal harm when administered to a pregnant woman [see Use in Specific Populations (8.1)].

Females

Advise females of reproductive potential to use effective contraception during treatment with CABOMETYX and for 4 months after the final dose.

Infertility

Females and Males

Based on findings in animals, CABOMETYX may impair fertility in females and males of reproductive potential [see Nonclinical Toxicology (13.1)].

8.4 Pediatric Use

The safety and effectiveness of CABOMETYX for the treatment of differentiated thyroid cancer (DTC) and neuroendocrine tumors (NETs) have been established in pediatric patients aged 12 years and older.

Use of CABOMETYX in pediatric patients aged 12 years and older with DTC and NETs is supported by evidence from adequate and well-controlled studies of CABOMETYX in adults with additional population pharmacokinetic data demonstrating that cabozantinib exposure is within the same range between adults and pediatric patients aged 12 years and older at the recommended dosages [see Dosage and Administration (2.2, 2.3), Adverse Reactions (6.1), Clinical Pharmacology (12.3) and Clinical Studies (14.3, 14.4)].

Physeal widening has been observed in children with open growth plates when treated with CABOMETYX. Based on the limited available data of the effects of CABOMETYX on longitudinal growth, physeal and longitudinal growth monitoring is recommended in children with open growth plates.

The safety and effectiveness of CABOMETYX in pediatric patients less than 12 years of age have not been established.

Juvenile Animal Toxicity Data

Juvenile rats were administered cabozantinib at doses of 1 or 2 mg/kg/day from Postnatal Day 12 (comparable to less than 2 years in humans) through Postnatal Day 35 or 70. Mortalities occurred at doses ≥1 mg/kg/day (approximately 0.16 times the clinical dose of 60 mg/day based on body surface area). Hypoactivity was observed at both doses tested on Postnatal Day 22. Targets were generally similar to those seen in adult animals, occurred at both doses, and included the kidney (nephropathy, glomerulonephritis), reproductive organs, gastrointestinal tract (cystic dilatation and hyperplasia in Brunner’s gland and inflammation of duodenum; and epithelial hyperplasia of colon and cecum), bone marrow (hypocellularity and lymphoid depletion), and liver. Tooth abnormalities and whitening as well as effects on bones including reduced bone mineral content and density, physeal hypertrophy, and decreased cortical bone also occurred at all dose levels. Recovery was not assessed at a dose of 2 mg/kg (approximately 0.32 times the clinical dose of 60 mg based on body surface area) due to high levels of mortality. At the low dose level, effects on bone parameters were partially resolved but effects on the kidney and epididymis/testis persisted after treatment ceased.

8.5 Geriatric Use

In CABOSUN and METEOR, 41% of 409 patients treated with CABOMETYX were age 65 years and older, and 8% were 75 years and older. In CELESTIAL, 49% of 467 patients treated with CABOMETYX were age 65 years and older, and 15% were 75 years and older. In COSMIC-311, 50% of 125 patients treated with CABOMETYX were age 65 years and older, and 12% were 75 years and older. In CABINET, 38% of 63 patients treated with CABOMETYX were age 65 years and older, and 5% were 75 years and older in the pNET cohort, and 55% of 132 patients treated with CABOMETYX were age 65 years and older, and 13% were 75 years and older in the epNET cohort [see Clinical Studies (14)].

No overall differences in safety or effectiveness were observed between these patients and younger patients.

Of the 320 patients with RCC treated with CABOMETYX in combination with nivolumab in CHECKMATE-9ER, 41% were 65 years or older and 9% were 75 years or older [see Clinical Studies (14.1)].

No overall difference in safety was reported between older and younger patients receiving both CABOMETYX and nivolumab.

8.6 Hepatic Impairment

Increased exposure to cabozantinib has been observed in patients with moderate (Child-Pugh B) hepatic impairment. Reduce the CABOMETYX dose in patients with moderate hepatic impairment. Avoid CABOMETYX in patients with severe hepatic impairment (Child-Pugh C), since it has not been studied in this population [see Dosage and Administration (2.2, 2.6), Clinical Pharmacology (12.3)].

8.7 Renal Impairment

No dosage adjustment is recommended in patients with mild or moderate renal impairment. There is no experience with CABOMETYX in patients with severe renal impairment [see Clinical Pharmacology (12.3)].

10 OVERDOSAGE

One case of overdosage was reported following administration of another formulation of cabozantinib; a patient inadvertently took twice the intended dose for 9 days. The patient suffered Grade 3 memory impairment, Grade 3 mental status changes, Grade 3 cognitive disturbance, Grade 2 weight loss, and Grade 1 increase in BUN. The extent of recovery was not documented.

11 DESCRIPTION

CABOMETYX is the (S)-malate salt of cabozantinib, a kinase inhibitor. Cabozantinib (S)-malate is described chemically as N-(4-(6,7-dimethoxyquinolin-4-yloxy)phenyl)-N'-(4-fluorophenyl)cyclopropane-1,1-dicarboxamide, (2S)-hydroxybutanedioate. The molecular formula is C28H24FN3O5•C4H6O5 and the molecular weight is 635.6 Daltons as malate salt. The chemical structure of cabozantinib (S)-malate salt is:

Cabozantinib (S)-malate salt is a white to off-white solid that is practically insoluble in aqueous media.

CABOMETYX (cabozantinib) tablets for oral use are supplied as film-coated tablets containing 20 mg, 40 mg, or 60 mg of cabozantinib, which is equivalent to 25 mg, 51 mg, or 76 mg of cabozantinib (S)-malate, respectively. CABOMETYX also contains the following inactive ingredients: microcrystalline cellulose, lactose anhydrous, hydroxypropyl cellulose, croscarmellose sodium, colloidal silicon dioxide, and magnesium stearate.

The film coating contains hypromellose, titanium dioxide, triacetin, and iron oxide yellow.

12 CLINICAL PHARMACOLOGY

12.1 Mechanism of Action

In vitro biochemical and/or cellular assays have shown that cabozantinib inhibits the tyrosine kinase activity of MET, VEGFR-1, -2 and -3, AXL, RET, ROS1, TYRO3, MER, KIT, TRKB, FLT-3, and TIE-2. These receptor tyrosine kinases are involved in both normal cellular function and pathologic processes such as oncogenesis, metastasis, tumor angiogenesis, drug resistance, and maintenance of the tumor microenvironment.

12.2 Pharmacodynamics

The exposure-response or safety relationship for cabozantinib is not fully characterized.

Cardiac Electrophysiology

The effect of cabozantinib on QTc interval was evaluated in a randomized, double-blinded, placebo-controlled trial in patients with medullary thyroid cancer administered a cabozantinib capsule formulation. A mean increase in QTcF of 10 - 15 ms was observed at 4 weeks after initiation. A concentration-QTc relationship could not be definitively established. Changes in cardiac wave form morphology or new rhythms were not observed. No patients in this study had a confirmed QTcF > 500 ms nor did any patients in METEOR, CABOSUN, CELESTIAL, CHECKMATE-9ER, COSMIC-311, or CABINET.

12.3 Pharmacokinetics

Repeat daily dosing of a cabozantinib capsule formulation for 19 days resulted in 4- to 5-fold mean cabozantinib accumulation (based on AUC) compared to a single dose administration; steady state was achieved by Day 15.

Absorption

Median time to peak cabozantinib concentrations (Tmax) ranged from 3 to 4 hours post-dose. A 19% increase in the Cmax of CABOMETYX compared to a cabozantinib capsule formulation was observed following a single 140 mg dose. A less than 10% difference in the AUC was observed between CABOMETYX and a cabozantinib capsule formulation [see Dosage and Administration (2.1)].

Food Effect

Cabozantinib Cmax and AUC increased by 41% and 57%, respectively, following a high-fat meal relative to fasted conditions in healthy subjects administered a single oral dose of a cabozantinib capsule formulation.

Distribution

The oral volume of distribution (Vz/F) of cabozantinib is approximately 319 L. Cabozantinib is highly protein bound in human plasma (≥99.7%).

Elimination

The predicted terminal half-life is approximately 99 hours and the clearance (CL/F) at steady-state is estimated to be 2.2 L/hr.

Metabolism

Cabozantinib is a substrate of CYP3A4 in vitro.

Excretion

Approximately 81% of the total administered radioactivity was recovered within a 48-day collection period following a single dose of radiolabeled ^14C-cabozantinib in healthy subjects. Approximately 54% was recovered in feces and 27% in urine. Unchanged cabozantinib accounted for 43% of the total radioactivity in feces and was not detectable in urine following a 72-hour collection.

Specific Populations

The following patient characteristics did not result in a clinically relevant difference in the pharmacokinetics of cabozantinib: age (32-86 years), sex, race (Whites and non-Whites), or mild to moderate renal impairment (eGFR ≥30 mL/min/1.73 m^2 as estimated by MDRD (modification of diet in renal disease equation)). The pharmacokinetics of cabozantinib is unknown in patients with eGFR <29 mL/min/1.73m^2 as estimated by MDRD equation or requiring dialysis.

Pediatric Patients

The systemic exposures to cabozantinib in pediatric patients 12 years and older at the recommended dosages are expected to be comparable to the exposure in adults at the dose of CABOMETYX 60 mg once daily.

Patients with Hepatic Impairment

Based on a population pharmacokinetic analysis of cabozantinib in healthy subjects and patients with cancer, no clinically significant differences in the mean cabozantinib exposure were observed between subjects with normal liver function (total bilirubin and AST ≤ULN) and those with mild hepatic impairment (total bilirubin ≤ULN and AST >ULN or total bilirubin >1 to 1.5x ULN and any AST value). In a dedicated pharmacokinetic study, cabozantinib exposure (AUC0-INF) increased by 63% in patients with moderate hepatic impairment (Child-Pugh B). Patients with severe hepatic impairment have not been studied [see Dosage and Administration (2.6), Use in Specific Populations (8.6)].

Drug Interaction Studies

Clinical Studies

CYP3A4 Inhibitors:

Administration of a strong CYP3A4 inhibitor, ketoconazole (400 mg daily for 27 days), with a cabozantinib capsule formulation to healthy subjects increased single-dose cabozantinib exposure (AUC0-INF) by 38%.

CYP3A4 Inducers:

Administration of a strong CYP3A4 inducer, rifampin (600 mg daily for 31 days), with a cabozantinib capsule formulation to healthy subjects decreased single-dose cabozantinib exposure (AUC0-INF) by 77%.

CYP2C8 Substrates:

No clinically-significant effect on single-dose rosiglitazone (a CYP2C8 substrate) exposure (Cmax and AUC) was observed when co-administered with a cabozantinib capsule formulation at steady-state concentrations.

Gastric Acid Reducing Agents:

No clinically-significant effect on cabozantinib exposure (AUC) was observed following co- administration of the proton pump inhibitor (PPI) esomeprazole (40 mg daily for 6 days) with a single 100 mg dose of a cabozantinib capsule formulation to healthy subjects.

In vitro Studies

CYP Enzymes:

Inhibition of CYP3A4 reduced the formation of the oxidative metabolite by >80%. Inhibition of CYP2C9 had a minimal effect on cabozantinib metabolite formation (i.e., a <20% reduction). Inhibition of CYP1A2, CYP2A6, CYP2B6, CYP2C8, CYP2C19, CYP2D6 and CYP2E1 had no effect on cabozantinib metabolite formation.

Although cabozantinib is an inhibitor of CYP2C8 in vitro, a clinical study of this potential interaction concluded that concurrent use did not result in a clinically relevant effect on CYP2C8 substrate exposure. Given this finding, other less sensitive substrates of pathways affected by cabozantinib in vitro (i.e., CYP2C9, CYP2C19, and CYP3A4) were not evaluated in a clinical study, because, although a clinically relevant exposure effect cannot be ruled out, it is unlikely. Cabozantinib does not inhibit CYP1A2 and CYP2D6 isozymes in vitro.

Cabozantinib is an inducer of CYP1A1 mRNA; however, the clinical relevance of this finding is unknown. Cabozantinib does not induce CYP1A2, CYP2B6, CYP2C8, CYP2C9, CYP2C19 or CYP3A4.

Transporters:

Cabozantinib is an inhibitor, but not a substrate, of P-gp transport activities and has the potential to increase concentrations of co-administered substrates of P-gp. The clinical relevance of this finding is unknown.

Cabozantinib is a substrate of MRP2 in vitro and MRP2 inhibitors have the potential to increase concentrations of cabozantinib. The clinical relevance of this finding is unknown.

13 NONCLINICAL TOXICOLOGY

13.1 Carcinogenesis, Mutagenesis, Impairment of Fertility

The carcinogenic potential of cabozantinib has been evaluated in two species: rasH2 transgenic mice and Sprague-Dawley rats. In the 2-year rat carcinogenicity study, once daily oral administration of cabozantinib resulted in a statistically significant increase in the incidence of malignant/complex malignant pheochromocytoma in combination with benign pheochromocytoma or in benign pheochromocytoma alone in male rats at a dose of 1 mg/kg (approximately 5 times the human exposure by AUC at the recommended 60 mg dose). Cabozantinib was not carcinogenic in a 26-week carcinogenicity study in rasH2 transgenic mice at a slightly higher exposure than the intended human therapeutic exposure.

Cabozantinib was not mutagenic in vitro in the bacterial reverse mutation (Ames) assay and was not clastogenic in both the in vitro cytogenetic assay using human lymphocytes or in the in vivo mouse micronucleus assay.

Based on nonclinical findings, male and female fertility may be impaired by treatment with CABOMETYX. In a fertility study in which cabozantinib was administered to male and female rats at doses of 1, 2.5, and 5 mg/kg/day, male fertility was significantly compromised at doses equal to or greater than 2.5 mg/kg/day (approximately 13-fold of human AUC at the recommended dose), with a decrease in sperm counts and reproductive organ weights. In females, fertility was significantly reduced at doses equal to or greater than 1 mg/kg/day (5-fold of human AUC at the recommended dose) with a significant decrease in the number of live embryos and a significant increase in pre- and post-implantation losses.

Observations of effects on reproductive tract tissues in general toxicology studies were supportive of effects noted in the dedicated fertility study and included hypospermia and absence of corpora lutea in male and female dogs in a 6-month repeat dose study at plasma exposures (AUC) approximately 0.5-fold (males) and <0.1-fold (females) of those expected in humans at the recommended dose. In addition, female rats administered 5 mg/kg/day for 14 days (approximately 9-fold of human AUC at the recommended dose) exhibited ovarian necrosis.

14 CLINICAL STUDIES

14.1 Renal Cell Carcinoma

Previously Treated with Anti-angiogenic Therapy

The efficacy of CABOMETYX was evaluated in METEOR (NCT01865747), a randomized (1:1), open-label, multicenter trial of CABOMETYX versus everolimus conducted in patients with advanced RCC who had received at least 1 prior anti-angiogenic therapy. Patients had to have a Karnofsky Performance Score (KPS) ≥70%. Patients were stratified by the number of prior VEGFR tyrosine kinase inhibitors (TKIs) and Memorial Sloan Kettering Cancer Center (MSKCC) Risk Group.

Patients were randomized to receive CABOMETYX (N=330) 60 mg orally once daily or everolimus (N=328) 10 mg orally once daily. The majority of the patients were male (75%), with a median age of 62 years. Sixty-nine percent (69%) received only one prior anti-angiogenic therapy. Patient distribution by MSKCC risk groups was 46% favorable (0 risk factors), 42% intermediate (1 risk factor), and 13% poor (2 or 3 risk factors). Fifty-four percent (54%) of patients had 3 or more organs with metastatic disease, including lung (63%), lymph nodes (62%), liver (29%), and bone (22%).

The main efficacy outcome measure was progression-free survival (PFS) assessed by a blinded independent radiology review committee among the first 375 subjects randomized. Other efficacy endpoints were objective response rate (ORR) and overall survival (OS) in the Intent-to- Treat (ITT) population. Tumor assessments were conducted every 8 weeks for the first 12 months, then every 12 weeks thereafter. Patients received treatment until disease progression or experiencing unacceptable toxicity. Patients on both arms who had disease progression could continue treatment at the discretion of the investigator.

Statistically significant improvements in PFS, OS, and ORR were demonstrated for CABOMETYX compared to everolimus. Efficacy results are presented in Tables 18 and 19 and Figures 1 and 2.

Table 18: Efficacy Results in METEOR (First 375 Randomized)
Endpoint | CABOMETYX | Everolimus
 | N = 187 | N = 188
Median PFS (95% CI), months | 7.4 (5.6, 9.1) | 3.8 (3.7, 5.4)
HR (95% CI), p-value [stratified log-rank test with prior VEGFR-targeting TKI therapy (1 vs 2 or more) and MSKCC prognostic criteria for previously treated patients with RCC (0 vs 1 vs 2 or 3) as stratification factors (per IVRS data)] | 0.58 (0.45, 0.74), p<0.0001

Figure 1: Kaplan-Meier Curves of Progression-Free Survival in METEOR (First 375 Randomized)

Table 19: Efficacy Results in METEOR (ITT)
Endpoint | CABOMETYX | Everolimus
 | N = 330 | N = 328
Median OS (95% CI), months | 21.4 (18.7, NE) | 16.5 (14.7, 18.8)
HR (95% CI), p-value [stratified log-rank test with prior VEGFR-targeting TKI therapy (1 vs 2 or more) and MSKCC prognostic criteria for previously treated patients with RCC (0 vs 1 vs 2 or 3) as stratification factors (per IVRS data)] | 0.66 (0.53, 0.83), p=0.0003
Confirmed ORR (partial responses only) (95% CI) | 17% (13%, 22%) | 3% (2%, 6%)
p-value [chi-squared test] | p<0.0001

Figure 2: Kaplan-Meier Curve of Overall Survival in METEOR (ITT)

First-line Treatment

CABOSUN

The efficacy of CABOMETYX was evaluated in CABOSUN (NCT01835158), a randomized (1:1), open-label, multicenter trial of CABOMETYX versus sunitinib conducted in patients with advanced RCC who had not received prior therapy. Patients were randomized to receive CABOMETYX (N=79) 60 mg orally once daily or sunitinib (N=78) 50 mg orally once daily (4 weeks on treatment followed by 2 weeks off) until disease progression or unacceptable toxicity. All patients were required to have intermediate or poor risk disease as defined by the International Metastatic RCC Database Consortium (IMDC) risk group categories. Patients were stratified by IMDC risk group and presence of bone metastases (yes/no).

The majority of patients were male (78%), with a median age of 63 years. Patient distribution by IMDC risk groups was 81% intermediate (1-2 risk factors) and 19% poor (≥3 risk factors). Thirty-six percent (36%) patients had bone metastases. Forty-six percent (46%) of patients were ECOG 0, 41% ECOG 1, and 13% ECOG 2.

The major efficacy outcome measure was progression-free survival (PFS) by a retrospective blinded independent radiology review committee (BIRC).

A statistically significant improvement in PFS, as assessed by a blinded independent radiology review committee, was demonstrated for CABOMETYX compared to sunitinib. Efficacy results are presented in Table 20, Figure 3, and Figure 4.

Table 20: Efficacy Results in CABOSUN
Endpoint | CABOMETYX | Sunitinib
 | N = 79 | N = 78
Progression-Free Survival [as assessed by a retrospective blinded independent radiology review committee (BIRC)]
Events, n(%) | 43 (54) | 49 (63)
Median PFS (95% CI), months | 8.6 (6.8, 14.0) | 5.3 (3.0, 8.2)
Hazard Ratio [estimated from stratified Cox proportional hazards model with stratification factors IMDC risk group and presence of bone metastases and treatment as covariate] (95% CI), p-value [two-sided stratified log-rank test with stratification factors IMDC risk group and presence of bone metastases] | 0.48 (0.31, 0.74), p=0.0008
Overall Survival
Events, n(%) | 43 (54) | 47 (60)
Hazard Ratio, [no multiplicity adjustments were made for overall survival or ORR] (95% CI) | 0.80 (0.53, 1.21)
Confirmed ORR, partial responses only (95% CI), | 20% (12.0, 30.8) | 9% (3.7, 17.6)

Figure 3: Kaplan-Meier Curve of Progression-Free Survival in CABOSUN

Figure 4: Kaplan-Meier Curve of Overall Survival in CABOSUN

CHECKMATE-9ER

CHECKMATE-9ER (NCT03141177) was a randomized, open-label study of CABOMETYX combined with nivolumab versus sunitinib in patients with previously untreated advanced RCC. CHECKMATE-9ER excluded patients with autoimmune disease or other medical conditions requiring systemic immunosuppression. Patients were stratified by IMDC prognostic score (favorable vs. intermediate vs. poor), PD-L1 tumor expression (≥1% vs. <1% or indeterminate), and region (US/Canada/Western Europe/Northern Europe vs. Rest of World).

Patients were randomized to CABOMETYX 40mg orally daily and nivolumab 240mg intravenously every 2 weeks (n=323), or sunitinib 50 mg orally daily for the first 4 weeks of a 6-week cycle (4 weeks on treatment followed by 2 weeks off) (n=328). Treatment continued until disease progression per RECIST v1.1 or unacceptable toxicity. Treatment beyond RECIST- defined disease progression was permitted if the patient was clinically stable and considered to be deriving clinical benefit by the investigator. Tumor assessments were performed at baseline, after randomization at Week 12, then every 6 weeks until Week 60, and then every 12 weeks thereafter.

The trial population characteristics were: median age 61 years (range: 28 to 90) with 38% ≥65 years of age and 10% ≥75 years of age. The majority of patients were male (74%) and White (82%) and 23% and 77% of patients had a baseline KPS of 70% to 80% and 90% to 100%, respectively. Patient distribution by IMDC risk categories was 22% favorable, 58% intermediate, and 20% poor.

The major efficacy outcome measure was PFS (BICR assessed). Additional efficacy outcome measures were OS and ORR (BICR assessed). The trial demonstrated a statistically significant improvement in PFS, OS, and ORR for patients randomized to CABOMETYX and nivolumab compared with sunitinib. Consistent results for PFS were observed across pre-specified subgroups of IMDC risk categories and PD-L1 tumor expression status. An updated efficacy analysis was conducted when 271 deaths were observed based on the pre-specified number of deaths for the pre-planned final analysis of OS. Efficacy results are shown in Table 21 and Figures 5 and 6.

Table 21: Efficacy Results in CHECKMATE-9ER
 | CABOMETYX and Nivolumab (n=323) | Sunitinib (n=328)
Progression-free Survival
Disease progression or deaths (%) | 144 (45) | 191 (58)
Median PFS (months) [Based on Kaplan-Meier estimates.] (95% CI) | 16.6 (12.5, 24.9) | 8.3 (7.0, 9.7)
Hazard ratio (95% CI) [Stratified Cox proportional hazards model.] | 0.51 (0.41, 0.64)
p-value [Based on stratified log-rank test] , [2-sided p-values from stratified log-rank test.] | <0.0001
Overall Survival
Deaths (%) | 67 (21) | 99 (30)
Median OS (months) (95% CI) | NR [Not Reached] | NR (22.6, NR)
Hazard ratio (95% CI) | 0.60 (0.40, 0.89)
p-value, , [p-value is compared with the allocated alpha of 0.0111 for this interim analysis.] | 0.0010
Updated Overall Survival
Deaths (%) | 121 (37) | 150 (46)
Median OS (months) (95% CI) | 37.7 (35.5, NR) | 34.3 (29.0, NR)
Hazard ratio (95% CI) | 0.70 (0.55, 0.90)
Confirmed Objective Response Rate (95% CI) [CI based on the Clopper and Pearson method.] | 55.7% (50.1, 61.2) | 27.1% (22.4, 32.3)
p-value [2-sided p-value from Cochran-Mantel-Haenszel test.] | <0.0001
Complete Response (CR) | 26 (8%) | 15 (4.6%)
Partial Response (PR) | 154 (48%) | 74 (23%)
Median duration of response in months (95% CI) | 20.2 (17.3, NR) | 11.5 (8.3, 18.4)

Figure 5: Kaplan-Meier Curve of Progression-Free Survival in CHECKMATE-9ER

Figure 6: Kaplan-Meier Curve of Updated Overall Survival in CHECKMATE-9ER

In an exploratory analysis, the updated analysis of OS in patients with IMDC favorable, intermediate, intermediate/poor, and poor risk demonstrated a HR (95% CI) of 1.03 (0.55, 1.92), 0.74 (0.54, 1.01), 0.65 (0.50, 0.85), and 0.49 (0.31, 0.79), respectively.

14.2 Hepatocellular Carcinoma

The efficacy of CABOMETYX was evaluated in CELESTIAL (NCT01908426), a randomized (2:1), double-blind, placebo-controlled, multicenter trial in patients with hepatocellular carcinoma (HCC) who had previously received sorafenib and had Child Pugh Class A liver impairment. Patients were randomized to receive CABOMETYX 60 mg orally once daily or placebo until disease progression or unacceptable toxicity. Randomization was stratified by etiology of disease (hepatitis B virus [HBV] with or without hepatitis C virus [HCV] vs. HCV [without HBV] vs. other [without HBV and HCV]), geographic region (Asia vs. other regions), and presence of extrahepatic spread of disease and/or macrovascular invasion (yes vs. no). The primary efficacy outcome measure was overall survival (OS). Additional outcome measures were progression-free survival (PFS) and objective response rate (ORR), as assessed by investigators per RECIST 1.1. Tumor assessments were conducted every 8 weeks.

In CELESTIAL, a total of 707 patients were randomized, 470 to CABOMETYX and 237 to placebo. The median age was 64 years (range 22 to 86 years), 82% were male, 56% were White and 34% were Asian. Baseline ECOG performance status was 0 (53%) or 1 (47%). The etiology of HCC was attributed to HBV in 38% of patients and HCV in 21%; etiology was attributed to causes other than HBV or HCV in 40%. Macroscopic vascular invasion or extra-hepatic tumor spread was present in 78% of patients and 41% had alpha-fetoprotein (AFP) levels ≥400 mcg/L. All patients received prior sorafenib and 27% received two prior systemic therapy regimens.

Efficacy results are summarized in Table 22, Figure 7, and Figure 8.

Table 22: Efficacy Results from CELESTIAL
Endpoint | CABOMETYX | Placebo
 | N = 470 | N = 237
Overall Survival
Number of Deaths, (%) | 317 (67) | 167 (70)
Median OS in Months (95% CI) | 10.2 (9.1, 12.0) | 8.0 (6.8, 9.4)
Hazard Ratio (95% CI) [estimated using the Cox proportional-hazard model] | 0.76 (0.63, 0.92)
p-value [log-rank test stratified by etiology of disease (HBV [with or without HCV], HCV [without HBV], or Other), geographic region (Asia, Other Regions), and presence of extrahepatic spread of disease and/or macrovascular invasion (Yes, No) as stratification factors (per IVRS data)] | p=0.0049 [significance level = 0.021 for 78% information (484 deaths) based on O’Brien-Fleming method]
Progression-Free Survival
Number of Events, (%) | 349 (74) | 205 (86)
Progressive Disease | 284 (60) | 186 (78)
Death | 65 (14) | 19 (8)
Median PFS in Months (95% CI) | 5.2 (4.0, 5.5) | 1.9 (1.9, 1.9)
Hazard Ratio (95% CI) | 0.44 (0.36, 0.52)
p-value | p<0.0001
Overall Response Rate (ORR)
Confirmed ORR (partial responses only) (95% CI) | 4% (2.3, 6.0) | 0.4% (0.0, 2.3)
p-value [Fisher’s exact test] | p=0.0086
CI, confidence interval

Figure 7: Kaplan-Meier Curve of Overall Survival in CELESTIAL

Figure 8: Kaplan-Meier Curve of Progression-Free Survival in CELESTIAL

14.3 Differentiated Thyroid Cancer

The efficacy of CABOMETYX was evaluated in COSMIC-311 (NCT03690388), a randomized (2:1), double-blind, placebo-controlled, multicenter trial in patients with locally advanced or metastatic differentiated thyroid cancer (DTC) that had progressed following prior VEGFR-targeted therapy and were radioactive iodine-refractory or ineligible. Patients were randomized to receive CABOMETYX 60 mg orally once daily or placebo with supportive care until disease progression or unacceptable toxicity. Randomization was stratified by prior receipt of lenvatinib (yes vs. no) and age (≤65 years vs >65 years). Eligible patients randomized to placebo were allowed to cross-over to CABOMETYX upon confirmation of progressive disease by blinded independent radiology review committee (BIRC). The multiple primary efficacy outcome measures were progression-free survival (PFS) in the ITT population, and overall response rate (ORR) in the first 100 randomized patients, as assessed by BIRC per RECIST 1.1. Tumor assessments were conducted every 8 weeks. Overall survival (OS) was a descriptive outcome measure.

The primary analysis of PFS included 187 randomized patients. An updated analysis of PFS was performed and included 258 randomized patients. The median age was 65 years (range 31 to 85 years), 53% were female, 70% were White, 19% were Asian, 2% were Black, 2% were American Indian or Alaska Native, and 63% received prior lenvatinib. Baseline ECOG performance status was 0 (46%) or 1 (54%) and 93% of patients had metastatic disease.

The trial demonstrated a statistically significant improvement in PFS, while it failed to demonstrate a statistically significant improvement in ORR, for patients randomized to CABOMETYX compared with placebo. Efficacy results are summarized in Table 23 and Figure 9.

Table 23: Efficacy Results from COSMIC-311
 | Primary Analysis |  | Updated Analysis [No formal statistical testing was conducted at the time of the updated analysis]
 | CABOMETYX (n=125) | Placebo (n=62) | CABOMETYX (n=170) | Placebo (n=88)
Progression-Free Survival
Number of Events, (%) | 31 (25) | 43 (69) | 62 (36) | 69 (78)
Median PFS in Months (95% CI) | NR (5.7, NE) | 1.9 (1.8, 3.6) | 11.0 (7.4, 13.8) | 1.9 (1.9, 3.7)
Hazard Ratio (95% CI) [Estimated using the Cox proportional-hazard model] | 0.22 (0.14, 0.35) |  | 0.22 (0.15, 0.31)
p-value [Log-rank test stratified by receipt of prior lenvatinib (yes vs no) and age (≤65 years vs >65 years)] | < 0.0001
Overall Response Rate (95% CI)
Overall Response, % (95% CI) [All responses were partial responses] , [The analysis population overall response rate was the first 100 randomized patients (67 in the CABOMETYX arm, and 33 in the placebo arm)] | 15% (7%, 26%) | 0% (0.0%, 11%) | 18% (10%, 29%) | 0% (0.0%, 11%)
p-value [Fisher’s exact test compared to an alpha boundary of 0.01] | 0.0281
CI, confidence interval; NR, not reached; NE, not evaluable

Figure 9: Kaplan-Meier Curve of Progression-Free Survival in COSMIC-311 (Updated Analysis, N=258)

14.4 Neuroendocrine Tumors

Pancreatic Neuroendocrine Tumors

The efficacy of CABOMETYX for the treatment of pancreatic neuroendocrine tumors (pNET) was evaluated in CABINET (NCT03375320), a randomized, double-blind, placebo-controlled, multicenter study in patients with unresectable, locally advanced or metastatic pNET that had progressed on prior therapy. Eligible patients were required to have been previously treated with at least one FDA approved therapy (everolimus, sunitinib, or lutetium Lu 177 dotatate), other than somatostatin analogs. Patients with active brain metastases or cranial epidural disease, and those who had prior treatment with cabozantinib were excluded. The study also excluded patients with clinically significant gastrointestinal (GI) bleeding, GI abnormalities, and tumor with invasion into the GI tract that may increase the risk for GI bleeding or perforation, and patients with tumor invading or encasing major blood vessels. Patients were randomized (2:1) to receive treatment with CABOMETYX 60 mg orally once daily or placebo until disease progression or unacceptable toxicity. Randomization was stratified by concurrent somatostatin analog (SSA) use (yes/no) and prior sunitinib therapy (yes/no). Tumor assessments were performed every 12 weeks. The study included patients with functional and non-functional tumors, and use of somatostatin analogs at a stable dose was permitted for symptom control. Eligible patients randomized to the placebo arm were allowed to crossover to CABOMETYX upon confirmation of progressive disease by blinded real time central review.

The major efficacy outcome measure was progression-free survival (PFS) assessed by blinded independent radiology review committee (BIRC) per RECIST 1.1. Additional efficacy outcome measures included overall response rate (ORR), duration of response (DOR) and overall survival (OS).

A total of 99 pNET patients were randomized (2:1) to receive CABOMETYX 60 mg orally once daily (n=66) or placebo (n=33). The median age was 60 years (range: 29 to 79); 57% were male; 83% were White, 6% Black or African American, 4.0% Asian, 1.0% American Indian or Alaska Native, 1.0% Native Hawaiian or other Pacific Islander, 1.0% multiple races, 4.0% not reported or unknown; and 5% were Hispanic or Latino. In the 99 patients with pNET, 27% had received one prior systemic therapy, 26% had received two prior systemic therapies and 46% had received three or more prior systemic therapies.

As recommended by the Data and Safety Monitoring Board, the CABINET study was unblinded prior to the final prespecified efficacy analysis and all patients remaining on the placebo arm were permitted to crossover to treatment with cabozantinib. At the time of unblinding, the trial demonstrated a statistically significant improvement in PFS assessed by BIRC for CABOMETYX compared to placebo. An updated OS analysis was conducted when 49 deaths were observed. OS data were not mature with 32 (48%) deaths in CABOMETYX arm and 17 (52%) deaths in placebo arm (OS HR=1.01 [95% CI: 0.55, 1.83]). Fifty-two percent of placebo arm patients crossed over to open label CABOMETYX, which may impact the OS endpoint.

Efficacy results are summarized in Table 24 and Figure 10.

Table 24: Efficacy Results in Patients with pNET in CABINET
 | CABOMETYX (N=66) | Placebo (N=33)
Progression-Free Survival (PFS)
Number of events (%) | 33 (50) | 26 (79)
Median (95% CI) [Kaplan-Meier method] , in months | 13.8 (8.9, 17.0) | 3.3 (2.8, 5.7)
Hazard Ratio (95% CI) [Stratified Cox proportional hazards model stratified by concurrent somatostatin analog (SSA) use (yes/no) and prior sunitinib therapy (yes/no)] | 0.22 (0.12, 0.41)
p-value [Stratified log-rank test stratified by concurrent somatostatin analog (SSA) use (yes/no) and prior sunitinib therapy (yes/no) (compared to one-sided alpha=0.001)] | <0.0001
Overall Response Rate (ORR)
ORR (95% CI) [Clopper-Pearson method] , % | 18 (10, 30) | 0 (0, 11)
Duration of Response (DOR)
Median (95% CI), in months | 11.4 (6.1, NE) | NE
CI, confidence interval; NE, not evaluable

Figure 10: Kaplan-Meier Curve of Progression-Free Survival in Patients with pNET in CABINET

Extra-Pancreatic Neuroendocrine Tumors

The efficacy of CABOMETYX for the treatment of extra-pancreatic neuroendocrine tumors (epNET) was evaluated in CABINET (NCT03375320), a randomized, double-blind, placebo- controlled, multicenter study in patients with unresectable, locally advanced or metastatic epNET that had progressed on prior therapy. Eligible patients were required to have been previously treated with at least one FDA approved therapy (everolimus or lutetium Lu 177 dotatate), other than somatostatin analogs. Patients with active brain metastases or cranial epidural disease, and those who had prior treatment with cabozantinib were excluded. The study also excluded patients with clinically significant gastrointestinal (GI) bleeding, GI abnormalities, and tumor with invasion into the GI tract that may increase the risk for GI bleeding or perforation, and patients with tumor invading or encasing major blood vessels. Patients were randomized (2:1) to receive treatment with CABOMETYX 60 mg orally once daily or placebo until disease progression or unacceptable toxicity. Randomization was stratified by concurrent somatostatin analog (SSA) use (yes/no) and primary site (midgut GI/unknown vs non-midgut GI/lung/other). Tumor assessments were performed every 12 weeks. The study included patients with functional and non-functional tumors, and use of somatostatin analogs at a stable dose was permitted for symptom control. Eligible patients randomized to the placebo arm were allowed to crossover to CABOMETYX upon confirmation of progressive disease by blinded real time central review.

The major efficacy outcome measure was progression-free survival (PFS) assessed by blinded independent radiology review committee (BIRC) per RECIST 1.1. Additional efficacy outcome measures included overall response rate (ORR), duration of response (DOR) and overall survival (OS).

A total of 199 epNET patients were randomized (2:1) to receive CABOMETYX 60 mg orally once daily (n=132) or placebo (n=67). The median age was 66 years (range: 28 to 86), 51% were female; 84% were White; 8% were Black or African American; 2.0% were Asian; 6% had race unknown or race not reported; and 8% were Hispanic or Latino. The primary sites of tumor were small bowel (34%) including duodenum, jejunum & ileum; lung (20%); thymus (5%); rectum (6%); cecum (2.0%); stomach (3.0%); non-cecum colon (1.0%); appendix (0.5%); others (18%); and unknown (12%). In the 199 patients with epNET, 46% had received one prior systemic therapy, 29% had received two prior systemic therapies and 25% had received three or more prior systemic therapies.

The trial demonstrated a statistically significant improvement in PFS as assessed by BIRC, for CABOMETYX compared to placebo. An updated OS analysis was conducted when 123 deaths were observed. OS data were not mature with 83 (63%) deaths in CABOMETYX arm and 40 (60%) deaths in placebo arm (OS HR=1.05 [95% CI: 0.71, 1.54]). Thirty-seven percent of placebo arm patients crossed over to open label CABOMETYX, which may impact the OS endpoint.

Efficacy results are summarized in Table 25 and Figure 11.

Table 25: Efficacy Results in Patients with epNET in CABINET
 | CABOMETYX (N=132) | Placebo (N=67)
Progression-Free Survival (PFS)
Number of events (%) | 68 (52) | 39 (58)
Median (95% CI) [Kaplan-Meier method] , in months | 8.5 (6.8, 12.5) | 4.2 (3.0, 5.7)
Hazard Ratio (95% CI) [Stratified Cox proportional hazards model stratified by concurrent somatostatin analog (SSA) use (yes/no) and primary site (midgut GI/unknown vs non-midgut GI/lung/other)] | 0.40 (0.26, 0.61)
p-value [Stratified log-rank test stratified by concurrent somatostatin analog (SSA) use (yes/no) and primary site (midgut GI/unknown vs non-midgut GI/lung/other) (compared to one-sided alpha=0.001)] | <0.0001
Overall Response Rate (ORR)
ORR (95% CI) [Clopper-Pearson method] , % | 5 (2.2, 11) | 0 (0, 5)
Duration of Response (DOR)
Median (95% CI), in months | 8.3 (4.5, NE) | NE
CI, confidence interval; NE, not evaluable

Figure 11: Kaplan-Meier Curve of Progression-Free Survival in Patients with epNET in CABINET

16 HOW SUPPLIED/STORAGE AND HANDLING

CABOMETYX tablets are supplied as follows:

60 mg tables are yellow film-coated, oval shaped with no score, debossed with "XL" on one side and "60" on the other side of the tablet; available in:
bottle of 30 tablets: NDC 42388-023-26
bottle of 30 tablets packaged in a carton: NDC 42388-023-46

40 mg tablets are yellow film-coated, triangle shaped with no score, debossed with "XL" on one side and "40" on the other side of the tablet; available in:
bottle of 30 tablets: NDC 42388-025-26
bottle of 30 tablets packaged in a carton: NDC 42388-025-46

20 mg tablets are yellow film-coated, round shaped with no score, debossed with "XL" on one side and "20" on the other side of the tablet; available in:
bottle of 30 tablets: NDC 42388-024-26
bottle of 30 tablets packaged in a carton: NDC 42388-024-46

Store CABOMETYX at 20°C to 25°C (68°F to 77°F); excursions are permitted from 15°C to 30°C (59°F to 86°F) [see USP Controlled Room Temperature].

17 PATIENT COUNSELING INFORMATION

Advise the patient to read the FDA-approved patient labeling (Patient Information).

- Hemorrhage: Instruct patients to contact their healthcare provider to seek immediate medical attention for signs or symptoms of unusual severe bleeding or hemorrhage [see Warnings and Precautions (5.1)].
- Perforations and fistulas: Advise patients that gastrointestinal disorders such as diarrhea, nausea, vomiting, and constipation may develop during CABOMETYX treatment and to seek immediate medical attention if they experience persistent or severe abdominal pain because cases of gastrointestinal perforation and fistula have been reported in patients taking CABOMETYX [see Warnings and Precautions (5.2)].
- Thromboembolic Events: Venous and arterial thromboembolic events have been reported. Advise patients to report signs or symptoms of an arterial thrombosis. Venous thromboembolic events including pulmonary embolus have been reported. Advise patients to contact their health care provider if new onset of dyspnea, chest pain, or localized limb edema occurs [see Warnings and Precautions (5.3)].
- Hypertension and hypertensive crisis: Inform patients of the signs and symptoms of hypertension. Advise patients to undergo routine blood pressure monitoring and to contact their health care provider if blood pressure is elevated or if they experience signs or symptoms of hypertension [see Warnings and Precautions (5.4)].
- Cardiac Failure: Advise patients that CABOMETYX can cause cardiac failure. Advise patients to immediately contact their healthcare provider for signs or symptoms of cardiac failure [see Warnings and Precautions (5.5)].
- Diarrhea: Advise patients to notify their healthcare provider at the first signs of poorly formed or loose stool or an increased frequency of bowel movements [see Warnings and Precautions (5.6)].
- Palmar-plantar erythrodysesthesia: Advise patients to contact their healthcare provider for progressive or intolerable rash [see Warnings and Precautions (5.7)].
- Hepatotoxicity: Advise patients to contact their healthcare provider immediately for jaundice, severe nausea or vomiting, or easy bruising or bleeding [see Warnings and Precautions (5.8)].
- Adrenal insufficiency: Advise patients receiving with nivolumab to contact their healthcare provider immediately for signs or symptoms of adrenal insufficiency [see Warnings and Precautions (5.9)].
- Proteinuria: Advise patients to contact their healthcare provider for signs or symptoms of proteinuria [see Warnings and Precautions (5.10)].
- Osteonecrosis of the jaw: Advise patients regarding good oral hygiene practices. Advise patients to immediately contact their healthcare provider for signs or symptoms associated with osteonecrosis of the jaw [see Warnings and Precautions (5.11)].
- Impaired wound healing: Advise patients that CABOMETYX may impair wound healing. Advise patients to inform their healthcare provider of any planned surgical procedure [see Dosage and Administration (2.1), Warnings and Precautions (5.12)].
- Reversible posterior leukoencephalopathy syndrome: Advise patients to immediately contact their health care provider for new onset or worsening neurological function [see Warnings and Precautions (5.13)].
- Thyroid dysfunction: Advise patients that CABOMETYX can cause thyroid dysfunction and that their thyroid function should be monitored regularly during treatment. Advise patients to immediately contact their healthcare provider for signs or symptoms of thyroid dysfunction [see Warnings and Precautions (5.14)].
- Hypocalcemia: Advise patients that CABOMETYX can cause low calcium levels and that their serum calcium levels should be monitored regularly during treatment. Advise patients to immediately contact their healthcare provider for signs or symptoms of hypocalcemia [see Warnings and Precautions (5.15)].
- Embryo-fetal toxicity:
  - Advise females of reproductive potential of the potential risk to a fetus. Advise females to inform their healthcare provider of a known or suspected pregnancy [see Warnings and Precautions (5.16), Use in Specific Populations (8.1)].
  - Advise females of reproductive potential to use effective contraception during treatment with CABOMETYX and for 4 months after the final dose [Use in Specific Populations (8.3)].
- Lactation: Advise women not to breastfeed during treatment with CABOMETYX and for 4 months following the last dose [Use in Specific Populations (8.2)].
- Drug interactions: Advise patients to inform their healthcare provider of all prescription or nonprescription medications, vitamins or herbal products. Inform patients to avoid grapefruit, grapefruit juice, and St. John’s wort [see Drug Interactions (7.1)].

Important administration information

- Instruct patients to take CABOMETYX on an empty stomach, at least 1 hour before or at least 2 hours after eating.

Manufactured for Exelixis, Inc. Alameda, CA 94502

PATIENT INFORMATION
CABOMETYX® (Ka-boe-met-iks)
cabozantinib
tablets

If your healthcare provider prescribes CABOMETYX in combination with nivolumab, also read the Medication Guide that comes with nivolumab.

What is CABOMETYX?
CABOMETYX is a prescription medicine used to treat:

- people with advanced kidney cancer (renal cell carcinoma). CABOMETYX may be used:
  - alone to treat people with renal cell carcinoma (RCC) that has spread (advanced RCC).
  - in combination with nivolumab when your cancer has spread (advanced RCC), and you have not already had treatment for your advanced RCC.
- people with liver cancer (hepatocellular carcinoma) who have been previously treated with the medicine sorafenib.
- adults and children 12 years of age and older who have a type of thyroid cancer called differentiated thyroid cancer (DTC), that has spread (locally advanced or metastatic), and,
  - has progressed after treatment with a VEGFR-targeted treatment, and
  - your DTC can no longer be treated with radioactive iodine, or you are not able to receive radioactive iodine treatment
- adults and children 12 years of age and older who have a type of cancer called pancreatic neuroendocrine tumors (pNET) or extra-pancreatic neuroendocrine tumors (epNET) that has been previously treated, cannot be treated by surgery, and has spread (locally advanced or metastatic).

It is not known if CABOMETYX is safe and effective in children younger than 12 years of age.

Before you take CABOMETYX, tell your healthcare provider about all of your medical conditions, including if you:

- have had a liver problem other than liver cancer
- have a recent history of bleeding, including coughing up or vomiting blood, or black tarry stools.
- have an open or healing wound
- have high blood pressure
- have heart problems
- have a low calcium level in your blood (hypocalcemia)
- plan to have any surgery, dental procedure, or have had a recent surgery. You should stop taking CABOMETYX at least 3 weeks before planned surgery. See "What are the possible side effects of CABOMETYX?"
- are pregnant, or plan to become pregnant. CABOMETYX can harm your unborn baby.
  - If you are able to become pregnant, your healthcare provider will check your pregnancy status before you start treatment with CABOMETYX.
  - Females who are able to become pregnant should use effective birth control (contraception) during treatment and for 4 months after your last dose of CABOMETYX.
  - Talk to your healthcare provider about birth control methods that may be right for you.
  - If you become pregnant or think you are pregnant, tell your healthcare provider right away.
- are breastfeeding or plan to breastfeed. It is not known if CABOMETYX passes into your breast milk. Do not breastfeed during treatment and for 4 months after your last dose of CABOMETYX.

Tell your healthcare provider about all the medicines you take, including prescription or over-the-counter medicines, vitamins, and herbal supplements. CABOMETYX and certain other medicines may affect each other causing side effects.

How should I take CABOMETYX?

- Take CABOMETYX exactly as your healthcare provider tells you to take it.
- Do not take CABOMETYX with food. Take CABOMETYX at least 1 hour before or at least 2 hours after eating.
- Swallow CABOMETYX tablets whole.
- Do not crush, chew or split CABOMETYX tablets.
- If you miss a dose and your next scheduled dose is in less than 12 hours, take your next dose at the normal time. Do not make up the missed dose.

What should I avoid while taking CABOMETYX?
Avoid drinking grapefruit juice, eating grapefruit or taking supplements that contain grapefruit or St. John’s wort during treatment with CABOMETYX.

What are the possible side effects of CABOMETYX?
CABOMETYX may cause serious side effects, including:

- bleeding (hemorrhage). CABOMETYX can cause severe bleeding that may lead to death. Tell your healthcare provider right away if you get any signs of bleeding during treatment with CABOMETYX, including:
  - coughing up blood or blood clots
  - vomiting blood or if your vomit looks like coffee-grounds
  - red or black (looks like tar) stools
  - menstrual bleeding that is heavier than normal
  - any unusual or heavy bleeding
- a tear in your stomach or intestinal wall (perforation) or an abnormal connection between 2 parts of your body (fistula). Tell your healthcare provider right away if you get tenderness or pain in your stomach-area (abdomen) that is severe or that does not go away.
- blood clots, stroke, heart attack, and chest pain. Get emergency help right away if you get:
  - swelling or pain in your arms or legs
  - shortness of breath
  - feel lightheaded or faint
  - sweating more than usual
  - numbness or weakness of your face, arm or leg, especially on one side of your body
  - sudden confusion, trouble speaking or understanding
  - sudden trouble seeing in one or both eyes
  - sudden trouble walking
  - dizziness, loss of balance or coordination
  - a sudden severe headache
- high blood pressure (hypertension). Hypertension is common with CABOMETYX and sometimes can be severe. Your healthcare provider will check your blood pressure before starting CABOMETYX and regularly during treatment with CABOMETYX. If needed, your healthcare provider may prescribe medicine to treat your high blood pressure. Tell your healthcare provider if you develop severe headaches, nose bleeds, tiredness or confusion, vision changes, chest pain, trouble breathing, irregular heartbeat, or blood in your urine.
- heart problems. CABOMETYX can cause heart failure that may lead to death. Your healthcare provider may check your heart function before and during treatment with CABOMETYX. Tell your healthcare provider right away if you get any of the following signs and symptoms:
  - feeling like your heart is pounding, racing, or beating irregularly
  - shortness of breath
  - swelling of your ankles or feet
  - feeling lightheaded
  - tiredness
- diarrhea. Diarrhea is common with CABOMETYX and can be severe. If needed, your healthcare provider may prescribe medicine to treat your diarrhea. Tell your healthcare provider right away if you have frequent loose, watery bowel movements.
- a skin problem called hand-foot skin reaction. Hand-foot skin reactions are common with CABOMETYX and can be severe. Tell your healthcare provider right away if you have rashes, redness, pain, swelling, or blisters on the palms of your hands or soles of your feet.
- liver problems. Liver problems may happen during treatment with CABOMETYX. When CABOMETYX is taken in combination with nivolumab, severe changes in liver function tests may happen more often than if you take CABOMETYX alone. Your healthcare provider will do blood tests to check your liver function before and during treatment with CABOMETYX. Tell your healthcare provider right away if you develop symptoms of liver problems including: yellowing of your skin or the whites of your eyes, severe nausea or vomiting, pain on the right side of your stomach-area (abdomen), dark urine, bleeding or bruising more easily than normal.
- adrenal gland problems. Your healthcare provider will monitor you for this problem. Your healthcare provider may prescribe hormone replacement therapy or corticosteroid medicines if needed. Tell your healthcare provider right away if you develop any of the following signs or symptoms: extreme tiredness, dizziness or fainting, weakness, nausea, or vomiting.
- protein in your urine and possible kidney problems. Symptoms may include swelling in your hands, arms, legs, or feet. Your healthcare provider will check you for this problem during treatment with CABOMETYX.
- severe jaw bone problems (osteonecrosis). Your healthcare provider should examine your mouth before you start and during treatment with CABOMETYX. Tell your dentist that you are taking CABOMETYX. It is important for you to practice good mouth care during treatment with CABOMETYX. Tell your healthcare provider right away if you develop any symptoms of jaw problems, including: jaw pain, toothache, or sores on your gums.
- wound healing problems. Wound healing problems have happened in some people who take CABOMETYX. Tell your healthcare provider if you plan to have any surgery before or during treatment with CABOMETYX.
  - You should stop taking CABOMETYX at least 3 weeks before planned surgery.
  - Your healthcare provider should tell you when you may start taking CABOMETYX again after surgery.
- Reversible Posterior Leukoencephalopathy Syndrome (RPLS). A condition called reversible posterior leukoencephalopathy syndrome can happen during treatment with CABOMETYX. Tell your healthcare provider right away if you have headaches, seizures, confusion, changes in vision, or problems thinking.
- change in thyroid function. CABOMETYX can cause changes in your thyroid function, including changes to thyroid hormone levels in your blood. Your healthcare provider will do blood tests to check your thyroid function before and during treatment with CABOMETYX.
- decreased calcium level in your blood (hypocalcemia). CABOMETYX can cause you to have a decreased amount of calcium in your blood. Your healthcare provider will do blood tests to check you for this problem and give you calcium if needed. Tell your healthcare provider right away if you get any of the following signs or symptoms:
  - muscle stiffness or muscle spasms
  - numbness or tingling in your fingers, toes, or around your mouth
  - seizures
  - sudden weight gain
  - swelling of your arms, hands, legs, and ankles

Your healthcare provider may change your dose, temporarily stop, or permanently stop treatment with CABOMETYX if you have certain side effects.
The most common side effects of CABOMETYX include:

- tiredness
- nausea and vomiting
- constipation
- decreased appetite
- weight decreased

The most common side effects of CABOMETYX when used in combination with nivolumab include:

- tiredness
- mouth sores
- rash
- low thyroid hormone levels (hypothyroidism)
- pain in muscles, bones, and joints
- decreased appetite
- nausea
- changes in the way things taste
- stomach-area (abdominal) pain
- cough
- upper respiratory tract infection

CABOMETYX may cause fertility problems in females and males, which may affect your ability to have children. Talk to your healthcare provider if you have concerns about fertility.
These are not all of the possible side effects of CABOMETYX. Call your doctor for medical advice about side effects. You may report side effects to FDA at 1-800-FDA-1088.

How should I store CABOMETYX?

- Store CABOMETYX at room temperature between 68°F to 77°F (20°C to 25°C).

Keep CABOMETYX and all medicines out of the reach of children.

General information about the safe and effective use of CABOMETYX.
Medicines are sometimes prescribed for purposes other than those listed in a Patient Information leaflet. Do not use CABOMETYX for a condition for which it was not prescribed. Do not give CABOMETYX to other people, even if they have the same symptoms you have. It may harm them.
You can ask your pharmacist or healthcare provider for information about CABOMETYX that is written for health professionals.

What are the ingredients in CABOMETYX?
Active ingredient: cabozantinib
Inactive ingredients: microcrystalline cellulose, lactose anhydrous, hydroxypropyl cellulose, croscarmellose sodium, colloidal silicon dioxide, and magnesium stearate. The film coating contains hypromellose, titanium dioxide, triacetin, and iron oxide yellow.
Manufactured for Exelixis, Inc. Alameda, CA 94502
For more information, go to www.cabometyx.com or call 1-855-292-3935.

This Patient Information has been approved by the U.S. Food and Drug Administration.

Revised: 10/2025

PACKAGE LABEL

Package Label - Bottle - 30 Tablets - 60mg CABOMETYX - Made in Canada

PRINCIPAL DISPLAY PANEL

NDC 42388-023-26

Cabometyx®
(cabozantinib) tablets
60 mg*

Rx Only
30 tablets
Exelixis®

PACKAGE LABEL

Package Label - Bottle - 30 Tablets - 40mg CABOMETYX - Made in Canada

PRINCIPAL DISPLAY PANEL

NDC 42388-025-26

Cabometyx®
(cabozantinib) tablets
40 mg*

Rx Only
30 tablets
Exelixis®

PACKAGE LABEL

Package Label - Bottle - 30 Tablets - 20mg CABOMETYX - Made in Canada

PRINCIPAL DISPLAY PANEL

NDC 42388-024-26

Cabometyx®
(cabozantinib) tablets
20 mg*

Rx Only
30 tablets
Exelixis®

PACKAGE LABEL

Package Label - Professional Sample - Bottle - 15 Tablets - 60mg CABOMETYX

PRINCIPAL DISPLAY PANEL

PROFESSIONAL SAMPLE - NOT FOR SALE

NDC 42388-023-37

Cabometyx®
(cabozantinib) tablets
60 mg*

Rx Only
15 tablets
Exelixis®

PACKAGE LABEL

Package Label - Professional Sample - Bottle - 15 Tablets - 40mg CABOMETYX

PRINCIPAL DISPLAY PANEL

PROFESSIONAL SAMPLE - NOT FOR SALE

NDC 42388-025-37

Cabometyx®
(cabozantinib) tablets
40 mg*

Rx Only
15 tablets
Exelixis®

PACKAGE LABEL

Package Label - Professional Sample - Bottle - 15 Tablets - 20mg CABOMETYX

PRINCIPAL DISPLAY PANEL

PROFESSIONAL SAMPLE - NOT FOR SALE

NDC 42388-024-37

Cabometyx®
(cabozantinib) tablets
20 mg*

Rx Only
15 tablets
Exelixis®

PACKAGE LABEL

Package Label - Bottle - 30 Tablets - 60mg CABOMETYX - Made in Germany

PRINCIPAL DISPLAY PANEL

NDC 42388-023-26

Cabometyx®
(cabozantinib) tablets
60 mg*

Rx Only
30 tablets
Exelixis®

PACKAGE LABEL

Package Label - Bottle - 30 Tablets - 40mg CABOMETYX - Made in Germany

PRINCIPAL DISPLAY PANEL

NDC 42388-025-26

Cabometyx®
(cabozantinib) tablets
40 mg*

Rx Only
30 tablets
Exelixis®

PACKAGE LABEL

Package Label - Bottle - 30 Tablets - 20mg CABOMETYX - Made in Germany

PRINCIPAL DISPLAY PANEL

NDC 42388-024-26

Cabometyx®
(cabozantinib) tablets
20 mg*

Rx Only
30 tablets
Exelixis®

PACKAGE LABEL

Package Carton - 30 Tablets - 60mg CABOMETYX - Made in Canada

PRINCIPAL DISPLAY PANEL

NDC 42388-023-46

Cabometyx®
(cabozantinib) tablets
60 mg*

Rx Only
30 tablets
Exelixis®

PACKAGE LABEL

Package Carton - 30 Tablets - 40mg CABOMETYX - Made in Canada

PRINCIPAL DISPLAY PANEL

NDC 42388-025-46

Cabometyx®
(cabozantinib) tablets
40 mg*

Rx Only
30 tablets
Exelixis®

PACKAGE LABEL

Package Carton - 30 Tablets - 20mg CABOMETYX - Made in Canada

PRINCIPAL DISPLAY PANEL

NDC 42388-024-46

Cabometyx®
(cabozantinib) tablets
20 mg*

Rx Only
30 tablets
Exelixis®

Package Carton - Professional Sample - 15 Tablets - 60mg CABOMETYX

PRINCIPAL DISPLAY PANEL

PROFESSIONAL SAMPLE - NOT FOR SALE

NDC 42388-023-57

Cabometyx®
(cabozantinib) tablets
60 mg*

Rx Only
15 tablets
Exelixis®

Package Carton - Professional Sample - 15 Tablets - 40mg CABOMETYX

PRINCIPAL DISPLAY PANEL

PROFESSIONAL SAMPLE - NOT FOR SALE

NDC 42388-025-57

Cabometyx®
(cabozantinib) tablets
40 mg*

Rx Only
15 tablets
Exelixis®

Package Carton - Professional Sample - 15 Tablets - 20mg CABOMETYX

PRINCIPAL DISPLAY PANEL

PROFESSIONAL SAMPLE - NOT FOR SALE

NDC 42388-024-57

Cabometyx®
(cabozantinib) tablets
20 mg*

Rx Only
15 tablets
Exelixis®

PACKAGE LABEL

Package Carton - 30 Tablets - 60mg CABOMETYX - Made in Germany

PRINCIPAL DISPLAY PANEL

NDC 42388-023-46

Cabometyx®
(cabozantinib) tablets
60 mg*

Rx Only
30 tablets
Exelixis®

PACKAGE LABEL

Package Carton - 30 Tablets - 40mg CABOMETYX - Made in Germany

PRINCIPAL DISPLAY PANEL

NDC 42388-025-46

Cabometyx®
(cabozantinib) tablets
40 mg*

Rx Only
30 tablets
Exelixis®

PACKAGE LABEL

Package Carton - 30 Tablets - 20mg CABOMETYX - Made in Germany

PRINCIPAL DISPLAY PANEL

NDC 42388-024-46

Cabometyx®
(cabozantinib) tablets
20 mg*

Rx Only
30 tablets
Exelixis®